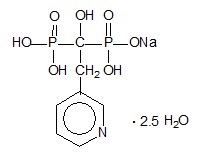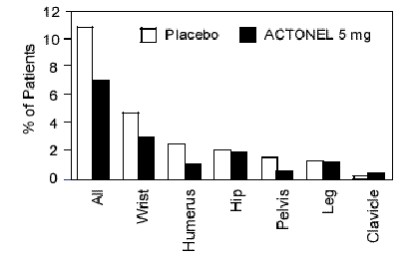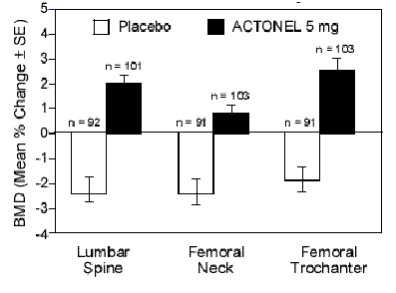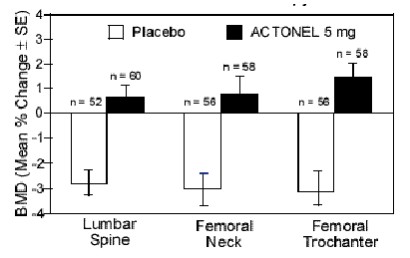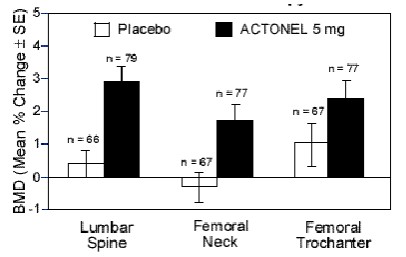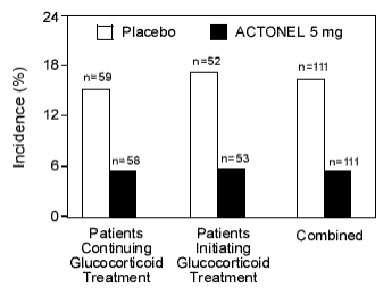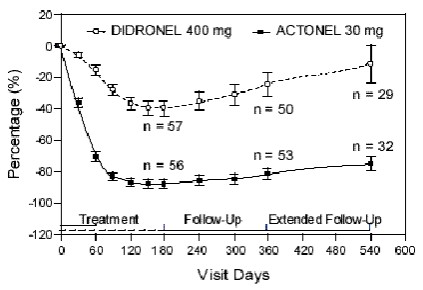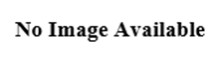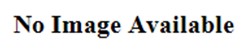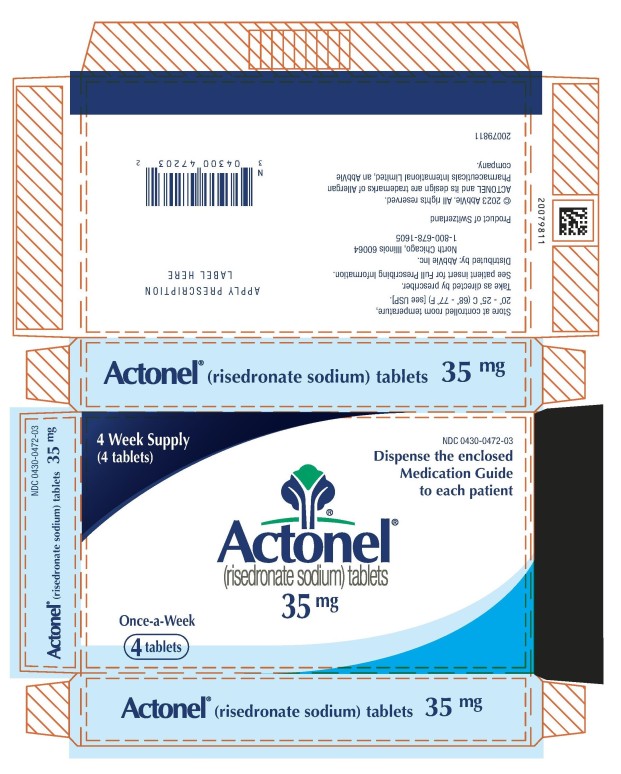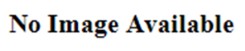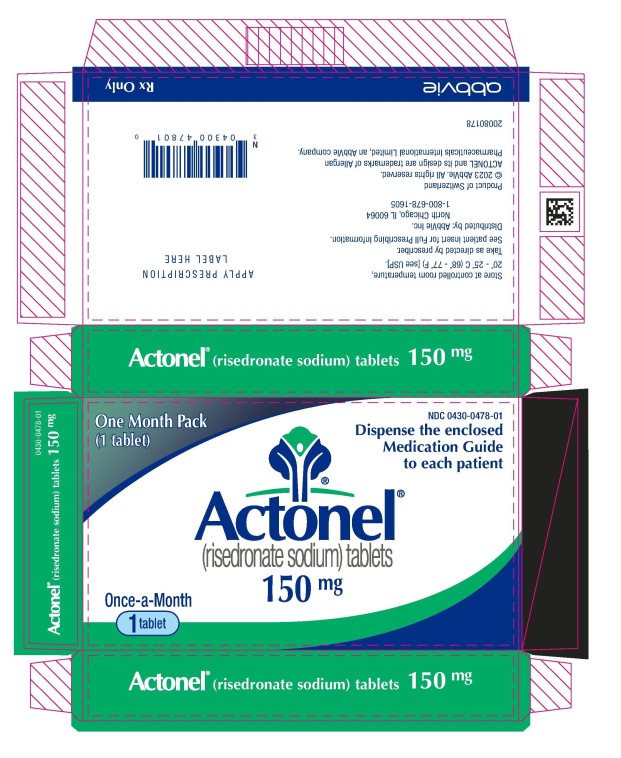 DRUG LABEL: Actonel
NDC: 0430-0471 | Form: TABLET, FILM COATED
Manufacturer: Allergan, Inc.
Category: prescription | Type: HUMAN PRESCRIPTION DRUG LABEL
Date: 20260203

ACTIVE INGREDIENTS: RISEDRONATE SODIUM HEMIPENTAHYDRATE 4.3 mg/1 1; RISEDRONATE SODIUM MONOHYDRATE 0.7 mg/1 1
INACTIVE INGREDIENTS: CROSPOVIDONE; HYDROXYPROPYL CELLULOSE (1600000 WAMW); HYPROMELLOSES; MAGNESIUM STEARATE; CELLULOSE, MICROCRYSTALLINE; POLYETHYLENE GLYCOL, UNSPECIFIED; SILICON DIOXIDE; TITANIUM DIOXIDE; FERRIC OXIDE YELLOW; LACTOSE MONOHYDRATE

HIGHLIGHTS OF PRESCRIBING INFORMATION

These highlights do not include all the information needed to use ACTONEL safely and effectively. See full prescribing information for ACTONEL.
ACTONEL® (risedronate sodium) tablets, for oral use
Initial U.S. Approval: 1998

RECENT MAJOR CHANGES

Warnings and Precautions, Atypical Fractures Including Femoral Fractures (5.6) | 02/2026

1 INDICATIONS AND USAGE

ACTONEL is a bisphosphonate indicated for:

- Treatment and prevention of postmenopausal osteoporosis (1.1)
- Treatment to increase bone mass in men with osteoporosis (1.2)
- Treatment and prevention of glucocorticoid-induced osteoporosis (1.3)
- Treatment of Paget’s disease (1.4)

Limitations of Use

Optimal duration of use has not been determined. For patients at low-risk for fracture, consider drug discontinuation after 3 to 5 years of use. (1.5)

2 DOSAGE AND ADMINISTRATION

Treatment of Postmenopausal Osteoporosis: 5 mg daily, 35 mg once-a-week, 75 mg two consecutive days each month, 150 mg once-a-month (2.1)

Prevention of Postmenopausal Osteoporosis: 5 mg daily, 35 mg once-a-week (2.2)

Men with Osteoporosis: 35 mg once-a-week (2.3)

Glucocorticoid-Induced Osteoporosis: 5 mg daily (2.4)

Paget’s Disease: 30 mg daily for 2 months (2.5)

Instruct patients to:

- Swallow tablet whole with 6 to 8 ounces of plain water, at least 30 minutes before the first food, beverage, or medication of the day
- Avoid lying down for 30 minutes (2)
- Take supplemental calcium and vitamin D if dietary intake is inadequate (2.7)

3 DOSAGE FORMS AND STRENGTHS

Tablets: 5, 30, 35, 75, and 150 mg (3)

4 CONTRAINDICATIONS

- Abnormalities of the esophagus which delay esophageal emptying such as stricture or achalasia (4, 5.1)
- Inability to stand or sit upright for at least 30 minutes (4, 5.1)
- Hypocalcemia (4, 5.3)
- Known hypersensitivity to any component of this product (4, 6.2)

5 WARNINGS AND PRECAUTIONS

- Products Containing Same Active Ingredient: Patients receiving Atelvia should not be treated with ACTONEL (5.1)
- Upper Gastrointestinal Adverse Reactions can occur. Instruct patients to follow dosing instructions. Discontinue use if new or worsening symptoms occur (5.2)
- Hypocalcemia may worsen and must be corrected prior to use (5.3)
- Osteonecrosis of the Jaw has been reported (5.4)
- Severe Bone, Joint, Muscle Pain may occur. Discontinue use if severe symptoms develop (5.5, 6.2)
- Atypical Fractures Including Femoral Fractures have been reported. Patients with new thigh or groin pain should be evaluated to rule out a femoral fracture. Risk/benefit of continuing bisphosphonate therapy should be re-evaluated in these patients and interruption of bisphosphonate therapy should be considered (5.6)

6 ADVERSE REACTIONS

Most common adverse reactions reported in greater than 10% of patients treated with ACTONEL and with a higher frequency than placebo are: back pain, arthralgia, abdominal pain, and dyspepsia (6.1)

Hypersensitivity reactions (angioedema, generalized rash, bullous skin reactions, Stevens-Johnson syndrome, and toxic epidermal necrolysis), and eye inflammation (iritis, uveitis) have been reported rarely (6.2)

To report SUSPECTED ADVERSE REACTIONS, contact AbbVie at 1-800-633-9110 or FDA at 1-800-FDA-1088 or www.fda.gov/medwatch.

7 DRUG INTERACTIONS

Calcium, antacids, or oral medications containing divalent cations interfere with the absorption of ACTONEL (7.1)

8 USE IN SPECIFIC POPULATIONS

- Pregnancy: Discontinue when pregnancy is recognized (8.1)
- ACTONEL is not recommended for use in patients with severe renal impairment (creatinine clearance less than 30 mL/min) (5.6, 8.6, 12.3)
- ACTONEL is not indicated for use in pediatric patients (8.4)

FULL PRESCRIBING INFORMATION

1 INDICATIONS AND USAGE

1.1 Postmenopausal Osteoporosis

ACTONEL is indicated for the treatment and prevention of osteoporosis in postmenopausal women. In postmenopausal women with osteoporosis, ACTONEL reduces the incidence of vertebral fractures and a composite endpoint of nonvertebral osteoporosis-related fractures [see Clinical Studies (14.1, 14.2)].

1.2 Osteoporosis in Men

ACTONEL is indicated for treatment to increase bone mass in men with osteoporosis.

1.3 Glucocorticoid-Induced Osteoporosis

ACTONEL is indicated for the treatment and prevention of glucocorticoid-induced osteoporosis in men and women who are either initiating or continuing systemic glucocorticoid treatment (daily dosage of greater than or equal to 7.5 mg of prednisone or equivalent) for chronic diseases. Patients treated with glucocorticoids should receive adequate amounts of calcium and vitamin D.

1.4 Paget’s Disease

ACTONEL is indicated for treatment of Paget’s disease of bone in men and women.

1.5 Important Limitations of Use

The optimal duration of use has not been determined. The safety and effectiveness of ACTONEL for the treatment of osteoporosis are based on clinical data of three years duration. All patients on bisphosphonate therapy should have the need for continued therapy re-evaluated on a periodic basis. Patients at low-risk for fracture should be considered for drug discontinuation after 3 to 5 years of use. Patients who discontinue therapy should have their risk for fracture re-evaluated periodically.

2 DOSAGE AND ADMINISTRATION

2.1 Treatment of Postmenopausal Osteoporosis

[see Indications and Usage (1.1)]

The recommended regimen is:

- one 5 mg tablet orally, taken daily
  or
- one 35 mg tablet orally, taken once-a-week
  or
- one 75 mg tablet orally, taken on two consecutive days for a total of two tablets each month
  or
- one 150 mg tablet orally, taken once-a-month

2.2 Prevention of Postmenopausal Osteoporosis

[see Indications and Usage (1.1)]

The recommended regimen is:

- one 5 mg tablet orally, taken daily
  or
- one 35 mg tablet orally, taken once-a-week
  or
- alternatively, one 75 mg tablet orally, taken on two consecutive days for a total of two tablets each month may be considered
  or
- alternatively, one 150 mg tablet orally, taken once-a-month may be considered

2.3 Treatment to Increase Bone Mass in Men with Osteoporosis

[see Indications and Usage (1.2)]

The recommended regimen is:

- one 35 mg tablet orally, taken once-a-week

2.4 Treatment and Prevention of Glucocorticoid-Induced Osteoporosis

[see Indications and Usage (1.3)]

The recommended regimen is:

- one 5 mg tablet orally, taken daily

2.5 Treatment of Paget’s Disease

[see Indications and Usage (1.4)]

The recommended treatment regimen is 30 mg orally once daily for 2 months. Retreatment may be considered (following post-treatment observation of at least 2 months) if relapse occurs, or if treatment fails to normalize serum alkaline phosphatase. For retreatment, the dose and duration of therapy are the same as for initial treatment. No data are available on more than 1 course of retreatment.

2.6 Important Administration Instructions

Instruct patients to do the following:

- Take ACTONEL at least 30 minutes before the first food or drink of the day other than water, and before taking any oral medication or supplementation, including calcium, antacids, or vitamins to maximize absorption and clinical benefit, [see Drug Interactions (7.1)]. Avoid the use of water with supplements, including mineral water, because they may have a higher concentration of calcium.
- Swallow ACTONEL tablets whole with a full glass of plain water (6 to 8 ounces). Avoid lying down for 30 minutes after taking the medication [see Warnings and Precautions (5.1)]. Do not chew or suck the tablet because of a potential for oropharyngeal ulceration.
- Do not eat or drink anything except plain water, or take other medications for at least 30 minutes after taking ACTONEL.

2.7 Recommendations for Calcium and Vitamin D Supplementation

Instruct patients to take supplemental calcium and vitamin D if their dietary intake is inadequate; and to take calcium supplements, antacids, magnesium-based supplements or laxatives, and iron preparations at a different time of the day as they interfere with the absorption of ACTONEL.

2.8 Administration Instructions for Missed Doses

Instruct patients about missing ACTONEL doses as follows:

- If a dose of ACTONEL 35 mg once-a-week is missed:
  - Take 1 tablet on the morning after they remember and return to taking 1 tablet once-a-week, as originally scheduled on their chosen day.
  - Do not take 2 tablets on the same day.

- If one or both tablets of ACTONEL 75 mg on two consecutive days per month are missed, and the next month’s scheduled doses are more than 7 days away:
  - If both tablets are missed, take one ACTONEL 75 mg tablet in the morning after the day it is remembered and then the other tablet on the next consecutive morning.
  - If only one ACTONEL 75 mg tablet is missed, take the missed tablet in the morning after the day it is remembered
  - Return to taking their ACTONEL 75 mg on two consecutive days per month as originally scheduled.
  - Do not take more than two 75 mg tablets within 7 days.

- If one or both tablets of ACTONEL 75 mg on two consecutive days per month are missed, and the next month's scheduled doses are within 7 days:
  - Wait until their next month’s scheduled doses and then continue taking ACTONEL 75 mg on two consecutive days per month as originally scheduled.

- If the dose of ACTONEL 150 mg once-a-month is missed, and the next month’s scheduled dose is more than 7 days away:
  - Take the missed tablet in the morning after the day it is remembered and then return to taking their ACTONEL 150 mg once-a-month as originally scheduled.
  - Do not take more than one 150 mg tablet within 7 days.

- If the dose of ACTONEL 150 mg once-a-month is missed, and the next month's scheduled dose is within 7 days:
  - Wait until their next month’s scheduled dose and then continue taking ACTONEL 150 mg once-a-month as originally scheduled.

3 DOSAGE FORMS AND STRENGTHS

- 5 mg film-coated, oval, yellow tablet with RSN on 1 face and 5 mg on the other.
- 30 mg film-coated, oval, white tablet with RSN on 1 face and 30 mg on the other.
- 35 mg film-coated, oval, orange tablet with RSN on 1 face and 35 mg on the other.
- 75 mg film-coated, oval, pink tablet with RSN on 1 face and 75 mg on the other.
- 150 mg film-coated, oval, blue tablet with RSN on 1 face and 150 mg on the other.

4 CONTRAINDICATIONS

ACTONEL is contraindicated in patients with the following conditions:

- Abnormalities of the esophagus which delay esophageal emptying such as stricture or achalasia [see Warnings and Precautions (5.1)]
- Inability to stand or sit upright for at least 30 minutes [see Dosage and Administration (2), Warnings and Precautions (5.1)]
- Hypocalcemia [see Warnings and Precautions (5.2)]
- Known hypersensitivity to ACTONEL or any of its excipients. Angioedema, generalized rash, bullous skin reactions, Stevens-Johnson syndrome and toxic epidermal necrolysis have been reported [see Adverse Reactions (6.2)]

5 WARNINGS AND PRECAUTIONS

5.1 Drug Products with the Same Active Ingredient

ACTONEL contains the same active ingredient found in Atelvia®. A patient being treated with Atelvia should not receive ACTONEL.

5.2 Upper Gastrointestinal Adverse Reactions

ACTONEL, like other bisphosphonates administered orally, may cause local irritation of the upper gastrointestinal mucosa. Because of these possible irritant effects and a potential for worsening of the underlying disease, caution should be used when ACTONEL is given to patients with active upper gastrointestinal problems (such as known Barrett’s esophagus, dysphagia, other esophageal diseases, gastritis, duodenitis or ulcers) [see Contraindications (4), Adverse Reactions (6.1), Information for Patients (17)].

Esophageal adverse experiences, such as esophagitis, esophageal ulcers and esophageal erosions, occasionally with bleeding and rarely followed by esophageal stricture or perforation, have been reported in patients receiving treatment with oral bisphosphonates. In some cases, these have been severe and required hospitalization. Physicians should therefore be alert to any signs or symptoms signaling a possible esophageal reaction and patients should be instructed to discontinue ACTONEL and seek medical attention if they develop dysphagia, odynophagia, retrosternal pain or new or worsening heartburn.

The risk of severe esophageal adverse experiences appears to be greater in patients who lie down after taking oral bisphosphonates and/or who fail to swallow it with the recommended full glass (6 to 8 ounces) of water, and/or who continue to take oral bisphosphonates after developing symptoms suggestive of esophageal irritation. Therefore, it is very important that the full dosing instructions are provided to, and understood by, the patient [see Dosage and Administration (2)]. In patients who cannot comply with dosing instructions due to mental disability, therapy with ACTONEL should be used under appropriate supervision.

There have been post-marketing reports of gastric and duodenal ulcers with oral bisphosphonate use, some severe and with complications, although no increased risk was observed in controlled clinical trials.

5.3 Mineral Metabolism

Hypocalcemia has been reported in patients taking ACTONEL. Treat hypocalcemia and other disturbances of bone and mineral metabolism before starting ACTONEL therapy. Instruct patients to take supplemental calcium and vitamin D if their dietary intake is inadequate. Adequate intake of calcium and vitamin D is important in all patients, especially in patients with Paget’s disease in whom bone turnover is significantly elevated [see Contraindications (4), Adverse Reactions (6.1), Information for Patients (17)].

5.4 Jaw Osteonecrosis

Osteonecrosis of the jaw (ONJ), which can occur spontaneously, is generally associated with tooth extraction and/or local infection with delayed healing, and has been reported in patients taking bisphosphonates, including ACTONEL. Known risk factors for osteonecrosis of the jaw include invasive dental procedures (for example, tooth extraction, dental implants, boney surgery), diagnosis of cancer, concomitant therapies (for example, chemotherapy, corticosteroids, angiogenesis inhibitors), poor oral hygiene, and co-morbid disorders (for example, periodontal and/or other pre-existing dental disease, anemia, coagulopathy, infection, ill-fitting dentures). The risk of ONJ may increase with duration of exposure to bisphosphonates.

For patients requiring invasive dental procedures, discontinuation of bisphosphonate treatment may reduce the risk for ONJ. Clinical judgment of the treating physician and/or oral surgeon should guide the management plan of each patient based on individual benefit/risk assessment.

Patients who develop osteonecrosis of the jaw while on bisphosphonate therapy should receive care by an oral surgeon. In these patients, extensive dental surgery to treat ONJ may exacerbate the condition. Discontinuation of bisphosphonate therapy should be considered based on individual benefit/risk assessment [see Adverse Reactions (6.2)].

5.5 Musculoskeletal Pain

In postmarketing experience, there have been reports of severe and occasionally incapacitating bone, joint, and/or muscle pain in patients taking bisphosphonates [see Adverse Reactions (6.2)]. The time to onset of symptoms varied from one day to several months after starting the drug. Most patients had relief of symptoms after stopping medication. A subset had recurrence of symptoms when rechallenged with the same drug or another bisphosphonate. Consider discontinuing use if severe symptoms develop.

5.6 Atypical Fractures Including Femoral Fractures

Atypical, low-energy, or low trauma fractures of the femoral shaft have been reported during treatment with bisphosphonates, including risedronate, in patients with osteoporosis. Atypical femur and other fractures most commonly occur with minimal or no trauma to the affected area. These fractures occurred anywhere in the femoral shaft from just below the lesser trochanter to above the supracondylar flare and are traverse or short oblique in orientation without evidence of comminution. Atypical fractures of other bones have also been reported. They may be bilateral. These fractures can also occur in osteoporotic patients who have not been treated with bisphosphonates. Concomitant treatment with glucocorticoids may also induce these fractures.

Prodromal pain in the affected area, usually presenting as dull, aching thigh pain, weeks to months before a complete fracture occurs was reported by patients.

Any patient with a history of bisphosphonate exposure who presents with thigh or groin pain should be suspected of having an atypical fracture and should be evaluated to rule out an incomplete femur fracture. Bony pain in other locations should also be considered for evaluation of atypical fracture. Patients presenting with an atypical fracture should also be assessed for symptoms and signs of fracture in the contralateral limb. Risk/benefit of continuing bisphosphonate therapy should be re-evaluated in these patients and interruption of bisphosphonate therapy should be considered.

5.7 Renal Impairment

ACTONEL is not recommended for use in patients with severe renal impairment (creatinine clearance less than 30 mL/min).

5.8 Glucocorticoid-Induced Osteoporosis

Before initiating ACTONEL treatment for the treatment and prevention of glucocorticoid-induced osteoporosis, the sex steroid hormonal status of both men and women should be ascertained and appropriate replacement considered.

5.9 Laboratory Test Interactions

Bisphosphonates are known to interfere with the use of bone-imaging agents. Specific studies with ACTONEL have not been performed.

6 ADVERSE REACTIONS

The following clinically significant adverse drug reactions are described elsewhere in the labeling:

- Drug Products with the Same Active Ingredient [see Warnings and Precautions (5.1)]
- Upper Gastrointestinal Adverse Reactions [see Warnings and Precautions (5.2)]
- Mineral Metabolism [see Warnings and Precautions (5.3)]
- Jaw Osteonecrosis [see Warnings and Precautions (5.4)]
- Musculoskeletal Pain [see Warnings and Precautions (5.5)]
- Atypical Fractures Including Femoral Fractures [see Warnings and Precautions (5.6)]
- Renal Impairment [see Warnings and Precautions (5.7)]
- Glucocorticoid-Induced Osteoporosis [see Warnings and Precautions (5.8)]
- Laboratory Test Interactions [see Warnings and Precautions (5.9)]

6.1 Clinical Studies Experience

Because clinical trials are conducted under widely varying conditions, adverse reaction rates observed in the clinical trials of a drug cannot be directly compared to rates in the clinical trials of another drug and may not reflect the rates observed in practice.

Treatment of Postmenopausal Osteoporosis

Daily Dosing

The safety of ACTONEL 5 mg once daily in the treatment of postmenopausal osteoporosis was assessed in four randomized, double-blind, placebo-controlled multinational trials of 3232 women aged 38 to 85 years with postmenopausal osteoporosis. The duration of the trials was up to three years, with 1619 patients exposed to placebo and 1613 patients exposed to ACTONEL 5 mg. Patients with pre-existing gastrointestinal disease and concomitant use of non-steroidal anti-inflammatory drugs, proton pump inhibitors, and H2 antagonists were included in these clinical trials. All women received 1000 mg of elemental calcium plus vitamin D supplementation up to 500 international units per day if their 25-hydroxyvitamin D3 level was below normal at baseline.

The incidence of all-cause mortality was 2.0% in the placebo group and 1.7% in the ACTONEL 5 mg daily group. The incidence of serious adverse events was 24.6% in the placebo group and 27.2% in the ACTONEL 5 mg group. The percentage of patients who withdrew from the study due to adverse events was 15.6% in the placebo group and 14.8% in the ACTONEL 5 mg group. The most common adverse reactions reported in greater than 10 percent of subjects were: back pain, arthralgia, abdominal pain and dyspepsia. Table 1 lists adverse events from the Phase 3 postmenopausal osteoporosis trials reported in greater than or equal to 5% of patients. Adverse events are shown without attribution of causality.

Table 1
Adverse Events Occurring at a Frequency greater than or equal to 5% in Either Treatment Group Combined Phase 3 Postmenopausal Osteoporosis Treatment Trials
Body System | Placebo N = 1619 | 5 mg ACTONEL N = 1613
 | % | %
Body as a Whole
Infection | 29.9 | 31.1
Back Pain | 26.1 | 28.0
Accidental Injury | 16.8 | 16.9
Pain | 14.0 | 14.1
Abdominal Pain | 9.9 | 12.2
Flu Syndrome | 11.6 | 10.5
Headache | 10.8 | 9.9
Asthenia | 4.5 | 5.4
Neck Pain | 4.7 | 5.4
Chest Pain | 5.1 | 5.0
Allergic Reaction | 5.9 | 3.8
Cardiovascular System
Hypertension | 9.8 | 10.5
Digestive System
Constipation | 12.6 | 12.9
Diarrhea | 10.0 | 10.8
Dyspepsia | 10.6 | 10.8
Nausea | 11.2 | 10.5
Metabolic & Nutritional Disorders
Peripheral Edema | 8.8 | 7.7
Musculoskeletal System
Arthralgia | 22.1 | 23.7
Arthritis | 10.1 | 9.6
Traumatic Bone Fracture | 12.3 | 9.3
Joint Disorder | 5.3 | 7.0
Myalgia | 6.2 | 6.7
Bone Pain | 4.8 | 5.3
Nervous System
Dizziness | 5.7 | 7.1
Depression | 6.1 | 6.8
Insomnia | 4.6 | 5.0
Respiratory System
Bronchitis | 10.4 | 10.0
Sinusitis | 9.1 | 8.7
Rhinitis | 5.1 | 6.2
Pharyngitis | 5.0 | 6.0
Increased Cough | 6.3 | 5.9
Skin and Appendages
Rash | 7.1 | 7.9
Special Senses
Cataract | 5.7 | 6.5
Urogenital System
Urinary Tract Infection | 10.4 | 11.1

Gastrointestinal Adverse Events:

The incidence of adverse events in the placebo and ACTONEL 5 mg daily groups were: abdominal pain (9.9% versus 12.2%), diarrhea (10.0% versus 10.8%), dyspepsia (10.6% versus 10.8%), and gastritis (2.3% versus 2.7%). Duodenitis and glossitis have been reported uncommonly in the ACTONEL 5 mg daily group (0.1% to 1%). In patients with active upper gastrointestinal disease at baseline, the incidence of upper gastrointestinal adverse events was similar between the placebo and ACTONEL 5 mg daily groups.

Musculoskeletal Adverse Events:

The incidence of adverse events in the placebo and ACTONEL 5 mg daily groups were: back pain (26.1% versus 28.0%), arthralgia (22.1% versus 23.7%), myalgia (6.2% versus 6.7%), and bone pain (4.8% versus 5.3%).

Laboratory Test Findings:

Throughout the Phase 3 studies, transient decreases from baseline in serum calcium (less than 1%) and serum phosphate (less than 3%) and compensatory increases in serum PTH levels (less than 30%) were observed within 6 months in patients in osteoporosis clinical trials treated with ACTONEL 5 mg once daily. There were no significant differences in serum calcium, phosphate, or PTH levels between placebo and ACTONEL 5 mg once daily at 3 years. Serum calcium levels below 8 mg/dL were observed in 18 patients, 9 (0.5%) in each treatment arm (placebo and ACTONEL 5 mg once daily). Serum phosphorus levels below 2 mg/dL were observed in 14 patients, 3 (0.2%) treated with placebo and 11 (0.6%) treated with ACTONEL 5 mg once daily. There have been rare reports (less than 0.1%) of abnormal liver function tests.

Endoscopic Findings:

In the ACTONEL clinical trials, endoscopic evaluation was encouraged in any patient with moderate-to-severe gastrointestinal complaints, while maintaining the blind. Endoscopies were performed on equal numbers of patients between the placebo and treated groups [75 (14.5%) placebo; 75 (11.9%) ACTONEL]. Clinically important findings (perforations, ulcers, or bleeding) among this symptomatic population were similar between groups (51% placebo; 39% ACTONEL).

Once-a-Week Dosing

The safety of ACTONEL 35 mg once-a-week in the treatment of postmenopausal osteoporosis was assessed in a 1-year, double-blind, multicenter study comparing ACTONEL 5 mg daily and ACTONEL 35 mg once-a-week in postmenopausal women aged 50 to 95 years. The duration of the trials was one year, with 480 patients exposed to ACTONEL 5 mg daily and 485 exposed to ACTONEL 35 mg once-a-week. Patients with pre-existing gastrointestinal disease and concomitant use of non-steroidal anti-inflammatory drugs, proton pump inhibitors, and H2 antagonists were included in these clinical trials. All women received 1000 mg of elemental calcium plus vitamin D supplementation up to 500 international units per day if their 25-hydroxyvitamin D3 level was below normal at baseline.

The incidence of all-cause mortality was 0.4% in the ACTONEL 5 mg daily group and 1.0% in the ACTONEL 35 mg once-a-week group. The incidence of serious adverse events was 7.1% in the ACTONEL 5 mg daily group and 8.2% in the ACTONEL 35 mg once-a-week group. The percentage of patients who withdrew from the study due to adverse events was 11.9% in the ACTONEL 5 mg daily group and 11.5% in the ACTONEL 35 mg once-a-week group. The overall safety and tolerability profiles of the two dosing regimens were similar.

Gastrointestinal Adverse Events:

The incidence of gastrointestinal adverse events was similar between the ACTONEL 5 mg daily group and the ACTONEL 35 mg once-a-week group: dyspepsia (6.9% versus 7.6%), diarrhea (6.3% versus 4.9%), and abdominal pain (7.3% versus 7.6%).

Musculoskeletal Adverse Events:

Arthralgia was reported in 11.5% of patients in the ACTONEL 5 mg daily group and 14.2% of patients in the ACTONEL 35 mg once-a-week group. Myalgia was reported by 4.6% of patients in the ACTONEL 5 mg daily group and 6.2% of patients in the ACTONEL 35 mg once-a-week group.

Laboratory Test Findings:

The mean percent changes from baseline at 12 months were similar between the ACTONEL 5 mg daily and ACTONEL 35 mg once-a-week groups, respectively, for serum calcium (0.4% versus 0.7%), phosphate (-3.8% versus -2.6%) and PTH (6.4% versus 4.2%).

Monthly Dosing

Two Consecutive Days per Month

The safety of ACTONEL 75 mg administered on two consecutive days per month for the treatment of postmenopausal osteoporosis was assessed in a double-blind, multicenter study in postmenopausal women aged 50 to 86 years. The duration of the trial was two years; 613 patients were exposed to ACTONEL 5 mg daily and 616 were exposed to ACTONEL 75 mg two consecutive days per month. Patients with pre-existing gastrointestinal disease and concomitant use of non-steroidal anti-inflammatory drugs, proton pump inhibitors, and H2 antagonists were included in this clinical trial. All women received 1000 mg of elemental calcium plus 400 to 800 international units of vitamin D supplementation per day.

The incidence of all-cause mortality was 1.0% for the ACTONEL 5 mg daily group and 0.5% for the ACTONEL 75 mg two consecutive days per month group. The incidence of serious adverse events was 10.8% in the ACTONEL 5 mg daily group and 14.4% in the ACTONEL 75 mg two consecutive days per month group. The percentage of patients who withdrew from treatment due to adverse events was 14.2% in the ACTONEL 5 mg daily group and 13.0% in the ACTONEL 75 mg two consecutive days per month group. The overall safety and tolerability profiles of the two dosing regimens were similar.

Acute Phase Reactions:

Symptoms consistent with acute phase reaction have been reported with bisphosphonate use. The overall incidence of acute phase reaction was 3.6% of patients on ACTONEL 5 mg daily and 7.6% of patients on ACTONEL 75 mg two consecutive days per month. These incidence rates are based on reporting of any of 33 acute phase reaction-like symptoms within 5 days of the first dose. Fever or influenza-like illness with onset within the same period were reported by 0.0% of patients on ACTONEL 5 mg daily and 0.6% of patients on ACTONEL 75 mg two consecutive days per month.

Gastrointestinal Adverse Events:

The ACTONEL 75 mg two consecutive days per month group resulted in a higher incidence of discontinuation due to vomiting (1.0% versus 0.2%) and diarrhea (1.0% versus 0.3%) compared to the ACTONEL 5 mg daily group. Most of these events occurred within a few days of dosing.

Ocular Adverse Events:

None of the patients treated with ACTONEL 75 mg two consecutive days per month reported ocular inflammation such as uveitis, scleritis, or iritis; 1 patient treated with ACTONEL 5 mg daily reported uveitis.

Laboratory Test Findings:

When ACTONEL 5 mg daily and ACTONEL 75 mg two consecutive days per month were compared in postmenopausal women with osteoporosis, the mean percent changes from baseline at 24 months were 0.2% and 0.8% for serum calcium, -1.9% and -1.3% for phosphate, and -10.4% and -17.2% for PTH, respectively. Compared to the ACTONEL 5 mg daily group, ACTONEL 75 mg two consecutive days per month resulted in a slightly higher incidence of hypocalcemia at the end of the first month of treatment (4.5% versus 3.0%). Thereafter, the incidence of hypocalcemia with these regimens was similar at approximately 2%.

Once-a-Month

The safety of ACTONEL 150 mg administered once-a-month for the treatment of postmenopausal osteoporosis was assessed in a double-blind, multicenter study in postmenopausal women aged 50 to 88 years. The duration of the trial was one year, with 642 patients exposed to ACTONEL 5 mg daily and 650 exposed to ACTONEL 150 mg once-a-month. Patients with pre-existing gastrointestinal disease and concomitant use of non-steroidal anti-inflammatory drugs, proton pump inhibitors, and H2 antagonists were included in this clinical trial. All women received 1000 mg of elemental calcium plus up to 1000 international units of vitamin D supplementation per day.

The incidence of all-cause mortality was 0.5% for the ACTONEL 5 mg daily group and 0.0% for the ACTONEL 150 mg once-a-month group. The incidence of serious adverse events was 4.2% in the ACTONEL 5 mg daily group and 6.2% in the ACTONEL 150 mg once-a-month group. The percentage of patients who withdrew from treatment due to adverse events was 9.5% in the ACTONEL 5 mg daily group and 8.6% in the ACTONEL 150 mg once-a-month group. The overall safety and tolerability profiles of the two dosing regimens were similar.

Acute Phase Reactions:

Symptoms consistent with acute phase reaction have been reported with bisphosphonate use. The overall incidence of acute phase reaction was 1.1% in the ACTONEL 5 mg daily group and 5.2% in the ACTONEL 150 mg once-a-month group. These incidence rates are based on reporting of any of 33 acute phase reaction-like symptoms within 3 days of the first dose and for a duration of 7 days or less. Fever or influenza-like illness with onset within the same period were reported by 0.2% of patients on ACTONEL 5 mg daily and 1.4% of patients on ACTONEL 150 mg once-a-month.

Gastrointestinal Adverse Events:

A greater percentage of patients experienced diarrhea with ACTONEL 150 mg once-a-month compared to 5 mg daily (8.2% versus 4.7%, respectively). The ACTONEL 150 mg once-a-month group resulted in a higher incidence of discontinuation due to abdominal pain upper (2.5% versus 1.4%) and diarrhea (0.8% versus 0.0%) compared to the ACTONEL 5 mg daily regimen. All of these events occurred within a few days of the first dose. The incidence of vomiting that led to discontinuation was the same in both groups (0.3% versus 0.3%).

Ocular Adverse Events:

None of the patients treated with ACTONEL 150 mg once-a-month reported ocular inflammation such as uveitis, scleritis, or iritis; 2 patients treated with ACTONEL 5 mg daily reported iritis.

Laboratory Test Findings:

When ACTONEL 5 mg daily and ACTONEL 150 mg once-a-month were compared in postmenopausal women with osteoporosis, the mean percent changes from baseline at 12 months were 0.1% and 0.3% for serum calcium, -2.3% and -2.3% for phosphate, and 8.3% and 4.8% for PTH, respectively. Compared to the ACTONEL 5 mg daily regimen, ACTONEL 150 mg once-a-month resulted in a slightly higher incidence of hypocalcemia at the end of the first month of treatment (0.2% versus 2.2%). Thereafter, the incidence of hypocalcemia with these regimens was similar at approximately 2%.

Prevention of Postmenopausal Osteoporosis

Daily Dosing

The safety of ACTONEL 5 mg daily in the prevention of postmenopausal osteoporosis was assessed in two randomized, double-blind, placebo-controlled trials. In one study of postmenopausal women aged 37 to 82 years without osteoporosis, the use of estrogen replacement therapy in both placebo- and ACTONEL-treated patients was included. The duration of the trial was one year, with 259 exposed to placebo and 261 patients exposed to ACTONEL 5 mg. The second study included postmenopausal women aged 44 to 63 years without osteoporosis. The duration of the trial was one year, with 125 exposed to placebo and 129 patients exposed to ACTONEL 5 mg. All women received 1000 mg of elemental calcium per day.

In the trial with estrogen replacement therapy, the incidence of all-cause mortality was 1.5% for the placebo group and 0.4% for the ACTONEL 5 mg group. The incidence of serious adverse events was 8.9% in the placebo group and 5.4% in the ACTONEL 5 mg group. The percentage of patients who withdrew from treatment due to adverse events was 18.9% in the placebo group and 10.3% in the ACTONEL 5 mg group. Constipation was reported by 1.9% of the placebo group and 6.5% of ACTONEL 5 mg group.

In the second trial, the incidence of all-cause mortality was 0.0% for both groups. The incidence of serious adverse events was 17.6% in the placebo group and 9.3% in the ACTONEL 5 mg group. The percentage of patients who withdrew from treatment due to adverse events was 6.4% in the placebo group and 5.4% in the ACTONEL 5 mg group. Nausea was reported by 6.4% of patients in the placebo group and 13.2% of patients in the ACTONEL 5 mg group.

Once-a-Week Dosing

There were no deaths in a 1-year, double-blind, placebo-controlled study of ACTONEL 35 mg once-a-week for prevention of bone loss in 278 postmenopausal women without osteoporosis. More treated subjects on ACTONEL reported arthralgia (placebo 7.8%; ACTONEL 13.9%), myalgia (placebo 2.1%; ACTONEL 5.1%), and nausea (placebo 4.3%; ACTONEL 7.3%) than subjects on placebo.

Treatment to Increase Bone Mass in Men with Osteoporosis

In a 2-year, double-blind, multicenter study, 284 men with osteoporosis were treated with placebo (N = 93) or ACTONEL 35 mg once-a-week (N = 191). The overall safety and tolerability profile of ACTONEL in men with osteoporosis was similar to the adverse events reported in the ACTONEL postmenopausal osteoporosis clinical trials, with the addition of benign prostatic hyperplasia (placebo 3%; ACTONEL 35 mg 5%), nephrolithiasis (placebo 0%; ACTONEL 35 mg 3%), and arrhythmia (placebo 0%; ACTONEL 35 mg 2%).

Treatment and Prevention of Glucocorticoid-Induced Osteoporosis

The safety of ACTONEL 5 mg daily in the treatment and prevention of glucocorticoid-induced osteoporosis was assessed in two randomized, double-blind, placebo-controlled multinational trials of 344 patients [male (123) and female (221)] aged 18 to 85 years who had recently initiated oral glucocorticoid therapy (less than or equal to 3 months, prevention study) or were on long-term oral glucocorticoid therapy (greater than or equal to 6 months, treatment study). The duration of the trials was one year, with 170 patients exposed to placebo and 174 patients exposed to ACTONEL 5 mg daily. Patients in one study received 1000 mg elemental calcium plus 400 international units of vitamin D supplementation per day; patients in the other study received 500 mg calcium supplementation per day.

The incidence of all-cause mortality was 2.9% in the placebo group and 1.1% in the ACTONEL 5 mg daily group. The incidence of serious adverse events was 33.5% in the placebo group and 30.5% in the ACTONEL 5 mg daily group. The percentage of patients who withdrew from the study due to adverse events was 8.8% in the placebo group and 7.5% in the ACTONEL 5 mg daily group. Back pain was reported in 8.8% of patients in the placebo group and 17.8% of patients in the ACTONEL 5 mg daily group. Arthralgia was reported in 14.7% of patients in the placebo group and 24.7% of patients in the ACTONEL 5 mg daily group.

Treatment of Paget’s Disease

ACTONEL has been studied in 392 patients with Paget’s disease of bone. As in trials of ACTONEL for other indications, the adverse experiences reported in the Paget’s disease trials have generally been mild or moderate, have not required discontinuation of treatment, and have not appeared to be related to patient age, gender, or race.

The safety of ACTONEL was assessed in a randomized, double-blind, active-controlled study of 122 patients aged 34 to 85 years. The duration of the trial was 540 days, with 61 patients exposed to ACTONEL and 61 patients exposed to Didronel®. The adverse event profile was similar for ACTONEL and Didronel: 6.6% (4/61) of patients treated with ACTONEL 30 mg daily for 2 months discontinued treatment due to adverse events, compared to 8.2% (5/61) of patients treated with Didronel 400 mg daily for 6 months. Table 2 lists adverse events reported in greater than or equal to 5% of ACTONEL-treated patients in Phase 3 Paget's disease trials. Adverse events shown are considered to be possibly or probably causally related in at least one patient.

Table 2
Adverse Events Reported in greater than or equal to 5% of ACTONEL-Treated Patients* in Phase 3 Paget's Disease Trials
Body System | 30 mg/day x 2 months ACTONEL % (N = 61) | 400 mg/day x 6 months Didronel % (N = 61)
Body as a Whole
Flu Syndrome | 9.8 | 1.6
Chest Pain | 6.6 | 3.3
Gastrointestinal
Diarrhea | 19.7 | 14.8
Abdominal Pain | 11.5 | 8.2
Nausea | 9.8 | 9.8
Constipation | 6.6 | 8.2
Metabolic and Nutritional Disorders
Peripheral Edema | 8.2 | 6.6
Musculoskeletal
Arthralgia | 32.8 | 29.5
Nervous
Headache | 18.0 | 16.4
Dizziness | 6.6 | 4.9
Skin and Appendages
Rash | 11.5 | 8.2
*Considered to be possibly or probably causally related in at least one patient.

Gastrointestinal Adverse Events:

During the first year of the study (treatment and nontreatment follow-up), the proportion of patients who reported upper gastrointestinal adverse events was similar between the treatment groups; no patients reported severe upper gastrointestinal adverse events. The incidence of diarrhea was 19.7% in the ACTONEL group and 14.8% in the Didronel group; none were serious or resulted in withdrawal.

Ocular Adverse Events:

Three patients who received ACTONEL 30 mg daily experienced acute iritis in 1 supportive study. All 3 patients recovered from their events; however, in 1 of these patients, the event recurred during ACTONEL treatment and again during treatment with pamidronate. All patients were effectively treated with topical steroids.

6.2 Postmarketing Experience

The following adverse reactions have been identified during post-approval use of ACTONEL or bisphosphonate products. Because these adverse reactions are reported voluntarily from a population of uncertain size, it is not always possible to reliably estimate their frequency or establish a causal relationship to drug exposure.

Hypersensitivity Reactions

Hypersensitivity and skin reactions have been reported, including angioedema, generalized rash, bullous skin reactions, Stevens-Johnson syndrome and toxic epidermal necrolysis.

Gastrointestinal Adverse Events

Events involving upper gastrointestinal irritation, such as esophagitis and esophageal or gastric ulcers, have been reported [see Warnings and Precautions (5.1)].

Musculoskeletal

Bone, joint, or muscle pain, described as severe or incapacitating, have been reported rarely [see Warnings and Precautions (5.4)]; low-energy femoral shaft and subtrochanteric fractures, and atypical fractures of other bones, [see Warnings and Precautions (5.6)].

Eye Inflammation

Reactions of eye inflammation including iritis and uveitis have been reported rarely.

Jaw Osteonecrosis

Osteonecrosis of the jaw has been reported rarely [see Warnings and Precautions (5.3)].

Pulmonary

Asthma exacerbations

7 DRUG INTERACTIONS

No specific drug-drug interaction studies were performed. Risedronate is not metabolized and does not induce or inhibit hepatic microsomal drug-metabolizing enzymes (for example, Cytochrome P450).

7.1 Calcium Supplements/Antacids

Co-administration of ACTONEL and calcium, antacids, or oral medications containing divalent cations will interfere with the absorption of ACTONEL.

7.2 Hormone Replacement Therapy

One study of about 500 early postmenopausal women has been conducted to date in which treatment with ACTONEL 5 mg daily plus estrogen replacement therapy was compared to estrogen replacement therapy alone. Exposure to study drugs was approximately 12 to 18 months and the primary endpoint was change in BMD. If considered appropriate, ACTONEL may be used concomitantly with hormone replacement therapy.

7.3 Aspirin/Nonsteroidal Anti-Inflammatory Drugs

Of over 5700 patients enrolled in the ACTONEL Phase 3 osteoporosis studies, aspirin use was reported by 31% of patients, 24% of whom were regular users (3 or more days per week). Forty-eight percent of patients reported NSAID use, 21% of whom were regular users. Among regular aspirin or NSAID users, the incidence of upper gastrointestinal adverse experiences in placebo-treated patients (24.8%) was similar to that in ACTONEL-treated patients (24.5%).

7.4 H 2 Blockers and Proton Pump Inhibitors (PPIs)

Of over 5700 patients enrolled in the ACTONEL Phase 3 osteoporosis studies, 21% used H2 blockers and/or PPIs. Among these patients, the incidence of upper gastrointestinal adverse experiences in the placebo-treated patients was similar to that in ACTONEL-treated patients.

8 USE IN SPECIFIC POPULATIONS

8.1 Pregnancy

Risk Summary

Available data on the use of ACTONEL in pregnant women are insufficient to inform a drug-associated risk of adverse maternal or fetal outcomes. Discontinue ACTONEL when pregnancy is recognized.

In animal reproduction studies, daily oral administration of risedronate to pregnant rats during organogenesis decreased neonatal survival and body weight at doses approximately 5 and 26 times, respectively, the highest recommended human daily dose of 30 mg (based on body surface area, mg/m^2). A low incidence of cleft palate was observed in fetuses of dams treated at doses approximately equal to the 30 mg human daily dose. Delayed skeletal ossification was observed in fetuses of dams treated at approximately 2.5 to 5 times the 30 mg human daily dose. Periparturient mortality due to maternal hypocalcemia occurred in dams and neonates upon daily oral administration of risedronate to pregnant rats during mating and/or gestation starting at doses equivalent to the 30 mg daily human dose.

Bisphosphonates are incorporated into the bone matrix, from which they are gradually released over a period of years. The amount of bisphosphonate incorporated into adult bone and available for release into the systemic circulation is directly related to the dose and duration of bisphosphonate use. Consequently, based on the mechanism of action of bisphosphonates, there is a potential risk of fetal harm, predominantly skeletal, if a woman becomes pregnant after completing a course of bisphosphonate therapy. The impact of variables such as time between cessation of bisphosphonate therapy to conception, the particular bisphosphonate used, and the route of administration (intravenous versus oral) on this risk has not been studied.

The estimated background risk of major birth defects and miscarriage for the indicated populations is unknown. All pregnancies have a background risk of birth defects, loss, or other adverse outcomes. In the U.S. general population, the estimated background risks of major birth defects and miscarriage in clinically recognized pregnancies is 2 - 4% and 15 - 20%, respectively.

Data

Animal Data

In animal studies, pregnant rats received risedronate sodium during organogenesis at doses equivalent to 1 to 26 times the 30 mg human daily dose (based on body surface area, mg/m^2). Survival of neonates was decreased in dams treated during gestation with oral doses approximately 5 times the human dose, and body weight was decreased in neonates of dams treated with approximately 26 times the human dose. A low incidence of cleft palate was observed in fetuses of dams treated with oral doses approximately equal to the human dose. The number of fetuses exhibiting incomplete ossification of sternebrae or skull of dams treated with approximately 2.5 times the human dose was significantly increased compared to controls. Both incomplete ossification and unossified sternebrae were increased in fetuses of dams treated with oral doses approximately 5 times the human dose.

No significant ossification effects were seen in fetuses of rabbits treated with oral doses approximately 7 times the human dose (the highest dose tested). However, 1 of 14 litters were aborted and 1 of 14 litters were delivered prematurely.

Periparturient mortality due to maternal hypocalcemia occurred in dams and neonates when pregnant rats were treated daily during mating and/or gestation with oral doses equivalent to the human dose or higher.

8.2 Lactation

Risk Summary

There are no data on the presence of risedronate in human milk, the effects on the breastfed infant, or the effects on milk production. A small degree of lacteal transfer occurred in nursing rats. The concentration of the drug in animal milk does not necessarily predict the concentration of drug in human milk. However, when a drug is present in animal milk, it is likely that the drug will be present in human milk. The developmental and health benefits of breastfeeding should be considered along with the mother’s clinical need for ACTONEL and any potential adverse effects on the breast-fed child from ACTONEL or from the underlying maternal condition.

Data

Animal Data

Risedronate was detected in neonates of lactating rats given a single oral dose of risedronate at 24-hours post-dosing, indicating a small degree of lacteal transfer.

8.4 Pediatric Use

ACTONEL is not indicated for use in pediatric patients.

The safety and effectiveness of risedronate was assessed in a one-year, randomized, double-blind, placebo-controlled study of 143 pediatric patients (94 received risedronate) with osteogenesis imperfecta (OI). The enrolled population was predominantly patients with mild osteogenesis imperfecta (85% Type-I), aged 4 to less than 16 years, 50% male and 82% Caucasian, with a mean lumbar spine BMD Z-score of -2.08 (2.08 standard deviations below the mean for age-matched controls). Patients received either a 2.5 mg (less than or equal to 30 kg body weight) or 5 mg (greater than 30 kg body weight) daily oral dose. After one year, an increase in lumbar spine BMD in the risedronate group compared to the placebo group was observed. However, treatment with risedronate did not result in a reduction in the risk of fracture in pediatric patients with osteogenesis imperfecta. In ACTONEL-treated subjects, no mineralization defects were noted in paired bone biopsy specimens obtained at baseline and month 12.

The overall safety profile of risedronate in OI patients treated for up to 12 months was generally similar to that of adults with osteoporosis. However, there was an increased incidence of vomiting compared to placebo. In this study, vomiting was observed in 15% of children treated with risedronate and 6% of patients treated with placebo. Other adverse events reported in greater than or equal to 10% of patients treated with risedronate and with a higher frequency than placebo were: pain in the extremity (21% with risedronate versus 16% with placebo), headache (20% versus 8%), back pain (17% versus 10%), pain (15% versus 10%), upper abdominal pain (11% versus 8%), and bone pain (10% versus 4%).

8.5 Geriatric Use

Of the patients receiving ACTONEL in postmenopausal osteoporosis studies [see Clinical Studies (14)], 47% were between 65 and 75 years of age, and 17% were over 75. The corresponding proportions were 26% and 11% in glucocorticoid-induced osteoporosis trials, and 40% and 26% in Paget’s disease trials. No overall differences in efficacy between geriatric and younger patients were observed in these studies. In the male osteoporosis trial, 28% of patients receiving ACTONEL were between 65 and 75 years of age and 9% were over 75. The lumbar spine BMD response for ACTONEL compared to placebo was 5.6% for subjects less than 65 years and 2.9% for subjects greater than or equal to 65 years. No overall differences in safety between geriatric and younger patients were observed in the ACTONEL trials, but greater sensitivity of some older individuals cannot be ruled out.

8.6 Renal Impairment

ACTONEL is not recommended for use in patients with severe renal impairment (creatinine clearance less than 30 mL/min) because of lack of clinical experience. No dosage adjustment is necessary in patients with a creatinine clearance greater than or equal to 30 mL/min.

8.7 Hepatic Impairment

No studies have been performed to assess risedronate’s safety or efficacy in patients with hepatic impairment. Risedronate is not metabolized in human liver preparations. Dosage adjustment is unlikely to be needed in patients with hepatic impairment.

10 OVERDOSAGE

Decreases in serum calcium and phosphorus following substantial overdose may be expected in some patients. Signs and symptoms of hypocalcemia may also occur in some of these patients. Milk or antacids containing calcium should be given to bind ACTONEL and reduce absorption of the drug.

In cases of substantial overdose, gastric lavage may be considered to remove unabsorbed drug. Standard procedures that are effective for treating hypocalcemia, including the administration of calcium intravenously, would be expected to restore physiologic amounts of ionized calcium and to relieve signs and symptoms of hypocalcemia.

Lethality after single oral doses was seen in female rats at 903 mg/kg and male rats at 1703 mg/kg. The minimum lethal dose in mice and rabbits was 4000 mg/kg and 1000 mg/kg, respectively. These values represent 320 to 620 times the 30 mg human dose based on surface area (mg/m^2).

11 DESCRIPTION

ACTONEL (risedronate sodium) tablets is a pyridinyl bisphosphonate that inhibits osteoclast-mediated bone resorption and modulates bone metabolism. Each ACTONEL tablet for oral administration contains the equivalent of 5, 30, 35, 75, or 150 mg of anhydrous risedronate sodium in the form of the hemi-pentahydrate with small amounts of monohydrate. The empirical formula for risedronate sodium hemi-pentahydrate is C7H10NO7P2Na •2.5 H2O. The chemical name of risedronate sodium is [1-hydroxy-2-(3-pyridinyl)ethylidene]bis[phosphonic acid] monosodium salt. The chemical structure of risedronate sodium hemi-pentahydrate is the following:

Molecular Weight:

Anhydrous: 305.10

Hemi-pentahydrate: 350.13

Risedronate sodium is a fine, white to off-white, odorless, crystalline powder. It is soluble in water and in aqueous solutions, and essentially insoluble in common organic solvents.

Inactive Ingredients

All dose strengths contain: crospovidone, hydroxypropyl cellulose, hypromellose, magnesium stearate, microcrystalline cellulose, polyethylene glycol, silicon dioxide, titanium dioxide.

Dose strength-specific ingredients include: 5 mg—ferric oxide yellow, lactose monohydrate; 30 mg—lactose monohydrate; 35 mg—ferric oxide red, ferric oxide yellow, lactose monohydrate; 75 mg—ferric oxide red; 150 mg—FD&C blue #2 aluminum lake.

12 CLINICAL PHARMACOLOGY

12.1 Mechanism of Action

ACTONEL has an affinity for hydroxyapatite crystals in bone and acts as an antiresorptive agent. At the cellular level, ACTONEL inhibits osteoclasts. The osteoclasts adhere normally to the bone surface, but show evidence of reduced active resorption (for example, lack of ruffled border). Histomorphometry in rats, dogs, and minipigs showed that ACTONEL treatment reduces bone turnover (activation frequency, that is, the rate at which bone remodeling sites are activated) and bone resorption at remodeling sites.

12.2 Pharmacodynamics

ACTONEL treatment decreases the elevated rate of bone turnover that is typically seen in postmenopausal osteoporosis. In clinical trials, administration of ACTONEL to postmenopausal women resulted in decreases in biochemical markers of bone turnover, including urinary deoxypyridinoline/creatinine and urinary collagen cross-linked N-telopeptide (markers of bone resorption) and serum bone-specific alkaline phosphatase (a marker of bone formation). At the 5 mg dose, decreases in deoxypyridinoline/creatinine were evident within 14 days of treatment. Changes in bone formation markers were observed later than changes in resorption markers, as expected, due to the coupled nature of bone resorption and bone formation; decreases in bone-specific alkaline phosphatase of about 20% were evident within 3 months of treatment. Bone turnover markers reached a nadir of about 40% below baseline values by the sixth month of treatment and remained stable with continued treatment for up to 3 years. Bone turnover is decreased as early as 14 days and maximally within about 6 months of treatment, with achievement of a new steady-state that more nearly approximates the rate of bone turnover seen in premenopausal women. In a 1-year study comparing daily versus weekly oral dosing regimens of ACTONEL for the treatment of osteoporosis in postmenopausal women, ACTONEL 5 mg daily and ACTONEL 35 mg once-a-week decreased urinary collagen cross-linked N-telopeptide by 60% and 61%, respectively. In addition, serum bone-specific alkaline phosphatase was also reduced by 42% and 41% in the ACTONEL 5 mg daily and ACTONEL 35 mg once-a-week groups, respectively. When postmenopausal women with osteoporosis were treated for 1 year with ACTONEL 5 mg daily or ACTONEL 75 mg two consecutive days per month, urinary collagen cross-linked N-telopeptide was decreased by 54% and 52%, respectively, and serum bone-specific alkaline phosphatase was reduced by 36% and 35%, respectively. In a 1–year study comparing ACTONEL 5 mg daily versus ACTONEL 150 mg once-a-month in women with postmenopausal osteoporosis, urinary collagen cross-linked N-telopeptide was decreased by 52% and 49%, respectively, and serum bone-specific alkaline phosphatase was reduced by 31% and 32%, respectively.

Osteoporosis in Men

In a 2-year study of men with osteoporosis, treatment with ACTONEL 35 mg once-a-week resulted in a mean decrease from baseline compared to placebo of 16% (placebo 20%; ACTONEL 35 mg 37%) for the bone resorption marker urinary collagen cross-linked N-telopeptide, 45% (placebo -6%; ACTONEL 35 mg 39%) for the bone resorption marker serum C-telopeptide, and 27% (placebo -2%; ACTONEL 35 mg 25%) for the bone formation marker serum bone-specific alkaline phosphatase.

Glucocorticoid-Induced Osteoporosis

Osteoporosis with glucocorticoid use occurs as a result of inhibited bone formation and increased bone resorption resulting in net bone loss. ACTONEL decreases bone resorption without directly inhibiting bone formation.

In two 1-year clinical trials in the treatment and prevention of glucocorticoid-induced osteoporosis, ACTONEL 5 mg decreased urinary collagen cross-linked N-telopeptide (a marker of bone resorption), and serum bone-specific alkaline phosphatase (a marker of bone formation) by 50% to 55% and 25% to 30%, respectively, within 3 to 6 months after initiation of therapy.

Paget’s Disease

Paget’s disease of bone is a chronic, focal skeletal disorder characterized by greatly increased and disordered bone remodeling. Excessive osteoclastic bone resorption is followed by osteoblastic new bone formation, leading to the replacement of the normal bone architecture by disorganized, enlarged, and weakened bone structure.

In pagetic patients treated with ACTONEL 30 mg daily for 2 months, bone turnover returned to normal in a majority of patients as evidenced by significant reductions in serum alkaline phosphatase (a marker of bone formation), and in urinary hydroxyproline/creatinine and deoxypyridinoline/creatinine (markers of bone resorption).

12.3 Pharmacokinetics

Absorption

Based on simultaneous modeling of serum and urine data, peak absorption after an oral dose is achieved at approximately 1 hour (Tmax) and occurs throughout the upper gastrointestinal tract. The fraction of the dose absorbed is independent of dose over the range studied (single dose, from 2.5 mg to 30 mg; multiple dose, from 2.5 mg to 5 mg). Steady-state conditions in the serum are observed within 57 days of daily dosing. Mean absolute oral bioavailability of the 30 mg tablet is 0.63% (90% CI: 0.54% to 0.75%) and is comparable to a solution.

Food Effect

The extent of absorption of a 30 mg dose (three 10 mg tablets) when administered 0.5 hours before breakfast is reduced by 55% compared to dosing in the fasting state (no food or drink for 10 hours prior to or 4 hours after dosing). Dosing 1 hour prior to breakfast reduces the extent of absorption by 30% compared to dosing in the fasting state. Dosing either 0.5 hours prior to breakfast or 2 hours after dinner (evening meal) results in a similar extent of absorption. ACTONEL is effective when administered at least 30 minutes before breakfast.

Distribution

The mean steady-state volume of distribution for risedronate is 13.8 L/kg in humans. Human plasma protein binding of drug is about 24%. Preclinical studies in rats and dogs dosed intravenously with single doses of [^14C] risedronate indicate that approximately 60% of the dose is distributed to bone. The remainder of the dose is excreted in the urine. After multiple oral dosing in rats, the uptake of risedronate in soft tissues was in the range of 0.001% to 0.01%.

Metabolism

There is no evidence of systemic metabolism of risedronate.

Excretion

In young healthy subjects, approximately half of the absorbed dose of risedronate was excreted in urine within 24 hours, and 85% of an intravenous dose was recovered in the urine over 28 days. Based on simultaneous modeling of serum and urine data, mean renal clearance was 105 mL/min (CV = 34%) and mean total clearance was 122 mL/min (CV = 19%), with the difference primarily reflecting nonrenal clearance or clearance due to adsorption to bone. The renal clearance is not concentration dependent, and there is a linear relationship between renal clearance and creatinine clearance. Unabsorbed drug is eliminated unchanged in feces. In osteopenic postmenopausal women, the terminal exponential half-life was 561 hours, mean renal clearance was 52 mL/min (CV = 25%), and mean total clearance was 73 mL/min (CV = 15%).

Specific Populations

Pediatric:

ACTONEL is not indicated for use in pediatric patients [see Pediatric Use (8.4)].

Gender:

Bioavailability and pharmacokinetics following oral administration are similar in men and women.

Geriatric:

Bioavailability and disposition are similar in elderly (greater than 60 years of age) and younger subjects. No dosage adjustment is necessary.

Race:

Pharmacokinetic differences due to race have not been studied.

Renal Impairment:

Risedronate is excreted unchanged primarily via the kidney. As compared to persons with normal renal function, the renal clearance of risedronate was decreased by about 70% in patients with creatinine clearance of approximately 30 mL/min. ACTONEL is not recommended for use in patients with severe renal impairment (creatinine clearance less than 30 mL/min) because of lack of clinical experience. No dosage adjustment is necessary in patients with a creatinine clearance greater than or equal to 30 mL/min.

Hepatic Impairment:

No studies have been performed to assess risedronate’s safety or efficacy in patients with hepatic impairment. Risedronate is not metabolized in rat, dog, and human liver preparations. Insignificant amounts (less than 0.1% of intravenous dose) of drug are excreted in the bile in rats. Therefore, dosage adjustment is unlikely to be needed in patients with hepatic impairment.

Drug Interactions:

No specific drug-drug interaction studies were performed. Risedronate is not metabolized and does not induce or inhibit hepatic microsomal drug-metabolizing enzymes (Cytochrome P450) [see Drug Interactions (7)].

13 NONCLINICAL TOXICOLOGY

13.1 Carcinogenesis, Mutagenesis, Impairment of Fertility

Carcinogenesis

In a 104-week carcinogenicity study, rats were administered daily oral doses up to approximately 8 times the maximum recommended human daily dose. There were no significant drug-induced tumor findings in male or female rats. The high dose male group was terminated early in the study (Week 93) due to excessive toxicity, and data from this group were not included in the statistical evaluation of the study results. In an 80-week carcinogenicity study, mice were administered daily oral doses approximately 6.5 times the human dose. There were no significant drug-induced tumor findings in male or female mice.

Mutagenesis

Risedronate did not exhibit genetic toxicity in the following assays: In vitro bacterial mutagenesis in Salmonella and E. coli (Ames assay), mammalian cell mutagenesis in CHO/HGPRT assay, unscheduled DNA synthesis in rat hepatocytes and an assessment of chromosomal aberrations in vivo in rat bone marrow. Risedronate was positive in a chromosomal aberration assay in CHO cells at highly cytotoxic concentrations (greater than 675 mcg/mL, survival of 6% to 7%). When the assay was repeated at doses exhibiting appropriate cell survival (29%), there was no evidence of chromosomal damage.

Impairment of Fertility

In female rats, ovulation was inhibited at an oral dose approximately 5 times the human dose. Decreased implantation was noted in female rats treated with doses approximately 2.5 times the human dose. In male rats, testicular and epididymal atrophy and inflammation were noted at approximately 13 times the human dose. Testicular atrophy was also noted in male rats after 13 weeks of treatment at oral doses approximately 5 times the human dose. There was moderate-to-severe spermatid maturation block after 13 weeks in male dogs at an oral dose approximately 8 times the human dose. These findings tended to increase in severity with increased dose and exposure time.

Dosing multiples provided above are based on the recommended human dose of 30 mg/day and normalized using body surface area (mg/m^2). Actual doses were 24 mg/kg/day in rats, 32 mg/kg/day in mice, and 8, 16 and 40 mg/kg/day in dogs.

13.2 Animal Toxicology and/or Pharmacology

Risedronate demonstrated potent anti-osteoclast, antiresorptive activity in ovariectomized rats and minipigs. Bone mass and biomechanical strength were increased dose-dependently at daily oral doses up to 4 and 25 times the human recommended oral dose of 5 mg for rats and minipigs, respectively. Risedronate treatment maintained the positive correlation between BMD and bone strength and did not have a negative effect on bone structure or mineralization. In intact dogs, risedronate induced positive bone balance at the level of the bone remodeling unit at oral doses ranging from 0.5 to 1.5 times the 5 mg/day human daily dose.

In dogs treated with an oral dose approximately 5 times the human daily dose, risedronate caused a delay in fracture healing of the radius. The observed delay in fracture healing is similar to other bisphosphonates. This effect did not occur at a dose approximately 0.5 times the human daily dose.

The Schenk rat assay, based on histologic examination of the epiphyses of growing rats after drug treatment, demonstrated that risedronate did not interfere with bone mineralization even at the highest dose tested, which was approximately 3500 times the lowest antiresorptive dose in this model (1.5 mcg/kg/day) and approximately 800 times the human daily dose of 5 mg. This indicates that ACTONEL administered at the therapeutic dose is unlikely to induce osteomalacia.

Dosing multiples provided above are based on the recommended human dose of 5 mg/day and normalized using body surface area (mg/m^2).

14 CLINICAL STUDIES

14.1 Treatment of Osteoporosis in Postmenopausal Women

The fracture efficacy of ACTONEL 5 mg daily in the treatment of postmenopausal osteoporosis was demonstrated in 2 large, randomized, placebo-controlled, double-blind studies that enrolled a total of almost 4000 postmenopausal women under similar protocols. The Multinational study (VERT MN) (ACTONEL 5 mg, N = 408) was conducted primarily in Europe and Australia; a second study was conducted in North America (VERT NA) (ACTONEL 5 mg, N = 821). Patients were selected on the basis of radiographic evidence of previous vertebral fracture, and therefore, had established disease. The average number of prevalent vertebral fractures per patient at study entry was 4 in VERT MN, and 2.5 in VERT NA, with a broad range of baseline BMD levels. All patients in these studies received supplemental calcium 1000 mg/day. Patients with low 25-hydroxyvitamin D3 levels (approximately 40 nmol/L or less) also received supplemental vitamin D 500 international units/day.

Effect on Vertebral Fractures

Fractures of previously undeformed vertebrae (new fractures) and worsening of pre-existing vertebral fractures were diagnosed radiographically; some of these fractures were also associated with symptoms (that is, clinical fractures). Spinal radiographs were scheduled annually and prospectively planned analyses were based on the time to a patient’s first diagnosed fracture. The primary endpoint for these studies was the incidence of new and worsening vertebral fractures across the period of 0 to 3 years. ACTONEL 5 mg daily significantly reduced the incidence of new and worsening vertebral fractures and of new vertebral fractures in both VERT NA and VERT MN at all time points (Table 3). The reduction in risk seen in the subgroup of patients who had 2 or more vertebral fractures at study entry was similar to that seen in the overall study population.

Table 3
The Effect of ACTONEL on the Risk of Vertebral Fractures
 | Proportion of Patients with Fracture (%)a
VERT NA | Placebo N = 678 | ACTONEL 5 mg N = 696 | Absolute Risk Reduction (%) | Relative Risk Reduction (%)
New and Worsening
0 - 1 Year | 7.2 | 3.9 | 3.3 | 49
0 - 2 Years | 12.8 | 8.0 | 4.8 | 42
0 - 3 Years | 18.5 | 13.9 | 4.6 | 33
New
0 - 1 Year | 6.4 | 2.4 | 4.0 | 65
0 - 2 Years | 11.7 | 5.8 | 5.9 | 55
0 - 3 Years | 16.3 | 11.3 | 5.0 | 41
VERT MN | Placebo N = 346 | ACTONEL 5 mg N = 344 | Absolute Risk Reduction (%) | Relative Risk Reduction (%)
New and Worsening
0 - 1 Year | 15.3 | 8.2 | 7.1 | 50
0 - 2 Years | 28.3 | 13.9 | 14.4 | 56
0 - 3 Years | 34.0 | 21.8 | 12.2 | 46
New
0 - 1 Year | 13.3 | 5.6 | 7.7 | 61
0 - 2 Years | 24.7 | 11.6 | 13.1 | 59
0 - 3 Years | 29.0 | 18.1 | 10.9 | 49
a Calculated by Kaplan-Meier methodology.

Effect on Osteoporosis-Related Nonvertebral Fractures

In VERT MN and VERT NA, a prospectively planned efficacy endpoint was defined consisting of all radiographically confirmed fractures of skeletal sites accepted as associated with osteoporosis. Fractures at these sites were collectively referred to as osteoporosis-related nonvertebral fractures. ACTONEL 5 mg daily significantly reduced the incidence of nonvertebral osteoporosis-related fractures over 3 years in VERT NA (8% versus 5%; relative risk reduction 39%) and reduced the fracture incidence in VERT MN from 16% to 11%. There was a significant reduction from 11% to 7% when the studies were combined, with a corresponding 36% reduction in relative risk. Figure 1 shows the overall results as well as the results at the individual skeletal sites for the combined studies.

Figure 1
Nonvertebral Osteoporosis-Related Fractures Cumulative Incidence Over 3 Years Combined VERT MN and VERT NA

Effect on Bone Mineral Density

The results of 4 randomized, placebo-controlled trials in women with postmenopausal osteoporosis (VERT MN, VERT NA, BMD MN, BMD NA) demonstrate that ACTONEL 5 mg daily increases BMD at the spine, hip, and wrist compared to the effects seen with placebo. Table 4 displays the significant increases in BMD seen at the lumbar spine, femoral neck, femoral trochanter, and midshaft radius in these trials compared to placebo. In both VERT studies (VERT MN and VERT NA), ACTONEL 5 mg daily produced increases in lumbar spine BMD that were progressive over the 3 years of treatment and were statistically significant relative to baseline and to placebo at 6 months and at all later time points.

Table 4
Mean Percent Increase in BMD from Baseline in Patients
Taking ACTONEL 5 mg or Placebo at Endpointa
 | VERT MNb |  | VERT NAb |  | BMD MNc |  | BMD NAc
 | Placebo N = 323 | 5 mg N = 323 | Placebo N = 599 | 5 mg N = 606 | Placebo N = 161 | 5 mg N = 148 | Placebo N = 191 | 5 mg N = 193
Lumbar Spine | 1.0 | 6.6 | 0.8 | 5.0 | 0.0 | 4.0 | 0.2 | 4.8
Femoral Neck | -1.4 | 1.6 | -1.0 | 1.4 | -1.1 | 1.3 | 0.1 | 2.4
Femoral Trochanter | -1.9 | 3.9 | -0.5 | 3.0 | -0.6 | 2.5 | 1.3 | 4.0
Midshaft Radius | -1.5* | 0.2* | -1.2* | 0.1* | ND |  | ND
aThe endpoint value is the value at the study's last time point for all patients who had BMD measured at that time; otherwise the last post-baseline BMD value prior to the study's last time point is used.
bThe duration of the studies was 3 years.
cThe duration of the studies was 1.5 to 2 years.
*BMD of the midshaft radius was measured in a subset of centers in VERT MN (placebo, N = 222; 5 mg, N = 214) and VERT NA (placebo, N = 310; 5 mg, N = 306).
ND = analysis not done

ACTONEL 35 mg once-a-week (N = 485) was shown to be non-inferior to ACTONEL 5 mg daily (N = 480) in a 1-year, double-blind, multicenter study of postmenopausal women with osteoporosis. In the primary efficacy analysis of completers, the mean increases from baseline in lumbar spine BMD at 1 year were 4.0% (3.7, 4.3; 95% confidence interval [CI]) in the 5 mg daily group (N = 391) and 3.9% (3.6, 4.3; 95% CI) in the 35 mg once-a-week group (N = 387) and the mean difference between 5 mg daily and 35 mg once-a-week was 0.1% (-0.4, 0.6; 95% CI). The results of the intent-to-treat analysis with the last observation carried forward were consistent with the primary efficacy analysis of completers. The 2 treatment groups were also similar with regard to BMD increases at other skeletal sites.

In a double-blind, multicenter study of postmenopausal women with osteoporosis, treatment with ACTONEL 75 mg two consecutive days per month (N = 616) was shown to be non-inferior to ACTONEL 5 mg daily (N = 613). In the primary efficacy analysis of completers, the mean increases from baseline in lumbar spine BMD at 1 year were 3.6% (3.3, 3.9; 95% CI) in the 5 mg daily group (N = 527) and 3.4% (3.1, 3.7; 95% CI) in the 75 mg two days per month group (N = 524) with a mean difference between groups being 0.2% (-0.2, 0.6; 95% CI). The results of the intent-to-treat analysis with the last observation carried forward were consistent with the primary efficacy analysis of completers. The 2 treatment groups were also similar with regard to BMD increases at other skeletal sites.

ACTONEL 150 mg once-a-month (N = 650) was shown to be non-inferior to ACTONEL 5 mg daily (N = 642) in a 1-year, double-blind, multicenter study of postmenopausal women with osteoporosis. The primary efficacy analysis was conducted in all randomized patients with baseline and post-baseline lumbar spine BMD values (modified intent-to-treat population) using last observation carried forward. The mean increases from baseline in lumbar spine BMD at 1 year were 3.4% (3.0, 3.8; 95% CI) in the 5 mg daily group (N = 561), and 3.5% (3.1, 3.9; 95% CI) in the 150 mg once-a-month group (N = 578) with a mean difference between groups being -0.1% (-0.5, 0.3; 95% CI). The results of the completers analysis were consistent with the primary efficacy analysis. The 2 treatment groups were also similar with regard to BMD increases at other skeletal sites.

Histology/Histomorphometry

Bone biopsies from 110 postmenopausal women were obtained at endpoint. Patients had received placebo or daily ACTONEL (2.5 mg or 5 mg) for 2 to 3 years. Histologic evaluation (N = 103) showed no osteomalacia, impaired bone mineralization, or other adverse effects on bone in ACTONEL-treated women. These findings demonstrate that bone formed during ACTONEL administration is of normal quality. The histomorphometric parameter mineralizing surface, an index of bone turnover, was assessed based upon baseline and post-treatment biopsy samples from 21 treated with placebo and 23 patients treated with ACTONEL 5 mg. Mineralizing surface decreased moderately in ACTONEL-treated patients (median percent change: placebo, -21%; ACTONEL 5 mg, -74%), consistent with the known effects of treatment on bone turnover.

Effect on Height

In the two 3-year osteoporosis treatment studies, standing height was measured yearly by stadiometer. Both ACTONEL and placebo-treated groups lost height during the studies. Patients who received ACTONEL had a statistically significantly smaller loss of height than those who received placebo. In VERT MN, the median annual height change was -2.4 mm/yr in the placebo group compared to -1.3 mm/yr in the ACTONEL 5 mg daily group. In VERT NA, the median annual height change was -1.1 mm/yr in the placebo group compared to -0.7 mm/yr in the ACTONEL 5 mg daily group.

14.2 Prevention of Osteoporosis in Postmenopausal Women

The safety and effectiveness of ACTONEL 5 mg daily for the prevention of postmenopausal osteoporosis were demonstrated in a 2-year, double-blind, placebo-controlled study of 383 postmenopausal women (age range 42 to 63 years) within three years of menopause (ACTONEL 5 mg, N = 129). All patients in this study received supplemental calcium 1000 mg/day. Increases in BMD were observed as early as 3 months following initiation of ACTONEL treatment. ACTONEL 5 mg daily produced significant mean increases in BMD at the lumbar spine, femoral neck, and trochanter compared to placebo at the end of the study (Figure 2). ACTONEL 5 mg daily was also effective in patients with lower baseline lumbar spine BMD (more than 1 SD below the premenopausal mean) and in those with normal baseline lumbar spine BMD. Bone mineral density at the distal radius decreased in both ACTONEL and placebo-treated women following 1 year of treatment.

Figure 2
Change in BMD from Baseline
2-Year Prevention Study

The safety and effectiveness of ACTONEL 35 mg once-a-week for the prevention postmenopausal osteoporosis were demonstrated in a 1-year, double-blind, placebo-controlled study of 278 patients (ACTONEL 35 mg, N = 136). All patients were supplemented with 1000 mg elemental calcium and 400 international units vitamin D per day. The primary efficacy measure was the percent change in lumbar spine BMD from baseline after 1 year of treatment using LOCF (last observation carried forward). ACTONEL 35 mg once-a-week resulted in a statistically significant mean difference from placebo in lumbar spine BMD of +2.9% (least square mean for placebo -1.05%; risedronate +1.83%). ACTONEL 35 mg once-a-week also showed a statistically significant mean difference from placebo in BMD at the total proximal femur of +1.5% (placebo -0.53%; risedronate +1.01%), femoral neck of +1.2% (placebo -1.00%; risedronate +0.22%), and trochanter of +1.8% (placebo -0.74%; risedronate +1.07%).

Combined Administration with Hormone Replacement Therapy

The effects of combining ACTONEL 5 mg daily with conjugated estrogen 0.625 mg daily (N = 263) were compared to the effects of conjugated estrogen alone (N = 261) in a 1-year, randomized, double-blind study of women ages 37 to 82 years, who were on average 14 years postmenopausal. The BMD results for this study are presented in Table 5.

Table 5
Percent Change from Baseline in BMD
After 1 Year of Treatment
 | Estrogen 0.625 mg N = 261 | ACTONEL 5 mg + Estrogen 0.625 mg N = 263
Lumbar Spine | 4.6 ± 0.20 | 5.2 ± 0.23
Femoral Neck | 1.8 ± 0.25 | 2.7 ± 0.25
Femoral Trochanter | 3.2 ± 0.28 | 3.7 ± 0.25
Midshaft Radius | 0.4 ± 0.14 | 0.7 ± 0.17
Distal Radius | 1.7 ± 0.24 | 1.6 ± 0.28
Values shown are mean (±SEM) percent change from baseline.

Histology/Histomorphometry

Bone biopsies from 53 postmenopausal women were obtained at endpoint. Patients had received ACTONEL 5 mg plus estrogen or estrogen-alone once daily for 1 year. Histologic evaluation (N = 47) demonstrated that the bone of patients treated with ACTONEL plus estrogen was of normal lamellar structure and normal mineralization. The histomorphometric parameter mineralizing surface, a measure of bone turnover, was assessed based upon baseline and post-treatment biopsy samples from 12 patients treated with ACTONEL plus estrogen and 12 treated with estrogen-alone. Mineralizing surface decreased in both treatment groups (median percent change: ACTONEL plus estrogen, -79%; estrogen-alone, -50%), consistent with the known effects of these agents on bone turnover.

14.3 Men with Osteoporosis

The effects of ACTONEL 35 mg once-a-week on BMD were examined in a 2-year, double-blind, placebo-controlled, multinational study in 285 men with osteoporosis (ACTONEL, N = 192). The patients had a mean age of 61 years (range 36 to 84 years) and 95% were Caucasian. At baseline, mean lumbar spine T-score was -3.2 and mean femoral neck T-score was -2.4. All patients in the study had either, 1) a BMD T-score less than or equal to -2 at the femoral neck and less than or equal to -1 at the lumbar spine, or 2) a BMD T-score less than or equal to -1 at the femoral neck and less than or equal to -2.5 at the lumbar spine. All patients were supplemented with calcium 1000 mg/day and vitamin D 400 to 500 international units/day. ACTONEL 35 mg once-a-week produced significant mean increases in BMD at the lumbar spine, femoral neck, trochanter, and total hip compared to placebo after 2 years of treatment (treatment difference: lumbar spine, 4.5%; femoral neck, 1.1%; trochanter, 2.2%; total proximal femur, 1.5%).

14.4 Glucocorticoid-Induced Osteoporosis

Bone Mineral Density

Two 1-year, double-blind, placebo-controlled trials in patients who were taking greater than or equal to 7.5 mg/day of prednisone or equivalent demonstrated that ACTONEL 5 mg daily was effective in the prevention and treatment of glucocorticoid-induced osteoporosis in men and women who were either initiating or continuing glucocorticoid therapy. The efficacy of ACTONEL therapy for glucocorticoid-induced osteoporosis beyond one year has not been studied.

The prevention study enrolled 228 patients (ACTONEL 5 mg, N = 76) (18 to 85 years of age), each of whom had initiated glucocorticoid therapy (mean daily dose of prednisone 21 mg) within the previous 3 months (mean duration of use prior to study 1.8 months) for rheumatic, skin, and pulmonary diseases. The mean lumbar spine BMD was normal at baseline (average T-score -0.7). All patients in this study received supplemental calcium 500 mg/day. By the third month of treatment, and continuing through the year-long treatment, the placebo group experienced losses in BMD at the lumbar spine, femoral neck, and trochanter, while BMD was maintained or increased in the ACTONEL 5 mg group. At each skeletal site there were statistically significant differences between the placebo group and the ACTONEL 5 mg group at all timepoints (Months 3, 6, 9, and 12). The treatment differences increased with continued treatment. Although BMD increased at the distal radius in the ACTONEL 5 mg group compared to the placebo group, the difference was not statistically significant. The differences between placebo and ACTONEL 5 mg after 1 year were 3.8% at the lumbar spine, 4.1% at the femoral neck, and 4.6% at the trochanter, as shown in Figure 3. The results at these skeletal sites were similar to the overall results when the subgroups of men and postmenopausal women, but not premenopausal women, were analyzed separately. ACTONEL was effective at the lumbar spine, femoral neck, and trochanter regardless of age (less than 65 vs. greater than or equal to 65), gender, prior and concomitant glucocorticoid dose, or baseline BMD. Positive treatment effects were also observed in patients taking glucocorticoids for a broad range of rheumatologic disorders, the most common of which were rheumatoid arthritis, temporal arteritis, and polymyalgia rheumatica.

The treatment study of similar design enrolled 290 patients (ACTONEL 5 mg, N = 100) (19 to 85 years of age) with continuing, long-term (greater than or equal to 6 months) use of glucocorticoids (mean duration of use prior to study 60 months; mean daily dose of prednisone 15 mg) for rheumatic, skin, and pulmonary diseases. The baseline mean lumbar spine BMD was low (1.63 SD below the young healthy population mean), with 28% of the patients more than 2.5 SD below the mean. All patients in this study received supplemental calcium 1000 mg/day and vitamin D 400 international units/day.

After 1 year of treatment, the BMD of the placebo group was within 1% of baseline levels at the lumbar spine, femoral neck, and trochanter. ACTONEL 5 mg increased BMD at the lumbar spine (2.9%), femoral neck (1.8%), and trochanter (2.4%). The differences between ACTONEL and placebo were 2.7% at the lumbar spine, 1.9% at the femoral neck, and 1.6% at the trochanter as shown in Figure 4. The differences were statistically significant for the lumbar spine and femoral neck, but not at the femoral trochanter. ACTONEL was similarly effective on lumbar spine BMD regardless of age (less than 65 vs. greater than or equal to 65), gender, or pre-study glucocorticoid dose. Positive treatment effects were also observed in patients taking glucocorticoids for a broad range of rheumatologic disorders, the most common of which were rheumatoid arthritis, temporal arteritis, and polymyalgia rheumatica.

Figure 3
Change in BMD from Baseline
Patients Recently Initiating
Glucocorticoid Therapy

Figure 4
Change in BMD from Baseline
Patients on Long-Term
Glucocorticoid Therapy

Vertebral Fractures

In the prevention study of patients initiating glucocorticoids, the incidence of vertebral fractures at 1 year was reduced from 17% in the placebo group to 6% in the ACTONEL group. In the treatment study of patients continuing glucocorticoids, the incidence of vertebral fractures was reduced from 15% in the placebo group to 5% in the ACTONEL group (Figure 5). The statistically significant reduction in vertebral fracture incidence in the analysis of the combined studies corresponded to an absolute risk reduction of 11% and a relative risk reduction of 70%. All vertebral fractures were diagnosed radiographically; some of these fractures also were associated with symptoms (that is, clinical fractures).

Figure 5
Incidence of Vertebral Fractures in Patients
Initiating or Continuing Glucocorticoid Therapy

Histology/Histomorphometry

Bone biopsies from 40 patients on glucocorticoid therapy were obtained at endpoint. Patients had received placebo or daily ACTONEL (2.5 mg or 5 mg) for 1 year. Histologic evaluation (N = 33) showed that bone formed during treatment with ACTONEL was of normal lamellar structure and normal mineralization, with no bone or marrow abnormalities observed. The histomorphometric parameter mineralizing surface, a measure of bone turnover, was assessed based upon baseline and post-treatment biopsy samples from 10 patients treated with ACTONEL 5 mg. Mineralizing surface decreased 24% (median percent change) in these patients. Only a small number of placebo-treated patients had both baseline and post-treatment biopsy samples, precluding a meaningful quantitative assessment.

14.5 Treatment of Paget’s Disease

The efficacy of ACTONEL was demonstrated in 2 clinical studies involving 120 men and 65 women. In a double-blind, active-controlled study of patients with moderate-to-severe Paget’s disease (serum alkaline phosphatase levels of at least 2 times the upper limit of normal), patients were treated with ACTONEL 30 mg daily for 2 months or Didronel (etidronate disodium) 400 mg daily for 6 months. At Day 180, 77% (43/56) of ACTONEL-treated patients achieved normalization of serum alkaline phosphatase levels, compared to 10.5% (6/57) of patients treated with Didronel (p less than 0.001). At Day 540, 16 months after discontinuation of therapy, 53% (17/32) of ACTONEL-treated patients and 14% (4/29) of Didronel-treated patients with available data remained in biochemical remission.

During the first 180 days of the active-controlled study, 85% (51/60) of ACTONEL-treated patients demonstrated a greater than or equal to 75% reduction from baseline in serum alkaline phosphatase excess (difference between measured level and midpoint of the normal range) with 2 months of treatment compared to 20% (12/60) in the Didronel-treated group with 6 months of treatment (p less than 0.001). Changes in serum alkaline phosphatase excess over time (shown in Figure 6) were significant following only 30 days of treatment, with a 36% reduction in serum alkaline phosphatase excess at that time compared to only a 6% reduction seen with Didronel treatment at the same time point (p less than 0.01).

Figure 6
Mean Percent Change from Baseline in
Serum Alkaline Phosphatase Excess by Visit

Response to ACTONEL therapy was similar in patients with mild to very severe Paget’s disease. Table 6 shows the mean percent reduction from baseline at Day 180 in excess serum alkaline phosphatase in patients with mild, moderate, or severe disease.

Table 6
Mean Percent Reduction from Baseline at Day 180 in
Total Serum Alkaline Phosphatase Excess by Disease Severity
 | ACTONEL 30 mg |  |  | Didronel 400 mg
Subgroup: Baseline Disease Severity (AP) | n | Baseline Serum AP (U/L)* | Mean % Reduction | n | Baseline Serum AP (U/L)* | Mean % Reduction
greater than 2, less than 3x ULN | 32 | 271.6 ± 5.3 | -88.1 | 22 | 277.9 ± 7.45 | -44.6
greater than or equal to 3, less than 7x ULN | 14 | 475.3 ± 28.8 | -87.5 | 25 | 480.5 ± 26.44 | -35.0
greater than or equal to 7x ULN | 8 | 1336.5 ± 134.19 | -81.8 | 6 | 1331.5 ± 167.58 | -47.2
*Values shown are mean ± SEM; ULN = upper limit of normal.

Response to ACTONEL therapy was similar between patients who had previously received anti-pagetic therapy and those who had not. In the active-controlled study, 4 patients previously non-responsive to 1 or more courses of anti-pagetic therapy (calcitonin, Didronel) responded to treatment with ACTONEL 30 mg daily (defined by at least a 30% change from baseline). Each of these patients achieved at least 90% reduction from baseline in serum alkaline phosphatase excess, with 3 patients achieving normalization of serum alkaline phosphatase levels.

Histomorphometry of the bone was studied in 14 patients with bone biopsies: 9 patients had biopsies from pagetic bone lesions and 5 patients from non-pagetic bone. Bone biopsy results in non-pagetic bone did not reveal osteomalacia, impairment of bone remodeling, or induction of a significant decline in bone turnover in patients treated with ACTONEL.

16 HOW SUPPLIED/STORAGE AND HANDLING

ACTONEL® is available as follows:

5 mg film-coated, oval, yellow tablets with RSN on 1 face and 5 mg on the other.
NDC 0430-0471-15 bottle of 30

30 mg film-coated, oval, white tablets with RSN on 1 face and 30 mg on the other.
NDC 0430-0470-15 bottle of 30

35 mg film-coated, oval, orange tablets with RSN on 1 face and 35 mg on the other.
NDC 0430-0472-03 dose pack of 4
NDC 0430-0472-07 dose pack of 12

75 mg film-coated, oval, pink tablets with RSN on 1 face and 75 mg on the other.
NDC 0430-0477-02 dose pack of 2

150 mg film-coated, oval, blue tablets with RSN on 1 face and 150 mg on the other.
NDC 0430-0478-01 dose pack of 1
NDC 0430-0478-02 dose pack of 3

Store at controlled room temperature 20° to 25° C (68° to 77° F) [see USP].

17 PATIENT COUNSELING INFORMATION

See FDA-approved patient labeling (Medication Guide)

Instruct patients to read the Medication Guide before starting therapy with ACTONEL and to re-read it each time the prescription is renewed.

Instruct patients that Atelvia and ACTONEL contain the same active ingredient and if they are taking Atelvia, they should not take ACTONEL [see Warnings and Precautions (5.1)].

Instruct patients to pay particular attention to the dosing instructions as clinical benefits may be compromised by failure to take the drug according to instructions. Specifically, ACTONEL should be taken at least 30 minutes before the first food or drink of the day other than water.

Instruct patients to take ACTONEL while in an upright position (sitting or standing) with a full glass of plain water (6 to 8 ounces) to facilitate delivery to the stomach, and thus reduce the potential for esophageal irritation.

Instruct patients not to lie down for 30 minutes after taking the medication [see Warnings and Precautions (5.1)].

Instruct patients not to chew or suck on the tablet because of a potential for oropharyngeal irritation.

Instruct patients that if they develop symptoms of esophageal disease (such as difficulty or pain upon swallowing, retrosternal pain or severe persistent or worsening heartburn) they should consult their physician before continuing ACTONEL.

Instruct patients about missing ACTONEL doses as follows:

- If a dose of ACTONEL 35 mg once-a-week is missed, they should take 1 tablet on the morning after they remember and return to taking 1 tablet once-a-week, as originally scheduled on their chosen day. Patients should not take 2 tablets on the same day.
- If one or both tablets of ACTONEL 75 mg on two consecutive days per month are missed, and the next month’s scheduled doses are more than 7 days away, the patient should be instructed as follows:
  - If both tablets are missed, take one ACTONEL 75 mg tablet in the morning after the day it is remembered and then the other tablet on the next consecutive morning.
  - If only one ACTONEL 75 mg tablet is missed, take the missed tablet in the morning after the day it is remembered.
  - Patients should then return to taking their ACTONEL 75 mg on two consecutive days per month as originally scheduled. Patients should not take more than two 75 mg tablets within 7 days.

- If one or both tablets of ACTONEL 75 mg on two consecutive days per month are missed, and the next month's scheduled doses are within 7 days, patients should wait until their next month’s scheduled doses and then continue taking ACTONEL 75 mg on two consecutive days per month as originally scheduled.
- If the dose of ACTONEL 150 mg once-a-month is missed, and the next month’s scheduled dose is more than 7 days away, the patient should be instructed to take the missed tablet in the morning after the day it is remembered. Patients should then return to taking their ACTONEL 150 mg once-a-month as originally scheduled. Patients should not take more than one 150 mg tablet within 7 days.
- If the dose of ACTONEL 150 mg once-a-month is missed, and the next month's scheduled dose is within 7 days, patients should wait until their next month’s scheduled dose and then continue taking ACTONEL 150 mg once-a-month as originally scheduled.

Instruct patients to take supplemental calcium and vitamin D if dietary intake is inadequate [see Warnings and Precautions (5.3)]. Weight-bearing exercise should be considered along with the modification of certain behavioral factors, such as excessive cigarette smoking, and/or alcohol consumption, if these factors exist.

Instruct patients to take calcium supplements or calcium-, aluminum-, and magnesium-containing medications at a different time of the day than ACTONEL as these medications may interfere with the absorption of ACTONEL.

Remind patients to give all of their healthcare providers an accurate medication history. Instruct patients to tell all of their healthcare providers that they are taking ACTONEL. Patients should be instructed that any time they have a medical problem they think may be from ACTONEL, they should talk to their doctor.

Distributed by:
AbbVie Inc.
North Chicago, Illinois 60064
© 2026 AbbVie. All rights reserved.
Actonel and its design are trademarks of Allergan Pharmaceuticals International Limited, an AbbVie company.

133169 R1

Medication Guide
ACTONEL® (AK-toh-nel)
(risedronate sodium)
Tablets

Read the Medication Guide that comes with ACTONEL® before you start taking it and each time you get a refill. There may be new information. This Medication Guide does not take the place of talking with your doctor about your medical condition or your treatment. Talk to your doctor if you have any questions about ACTONEL, there may be new information about it.

What is the most important information I should know about ACTONEL?

ACTONEL can cause serious side effects including:

1. Esophagus problems
2. Low calcium levels in your blood (hypocalcemia)
3. Severe jaw bone problems (osteonecrosis)
4. Bone, joint, or muscle pain
5. Unusual breaks in thigh and other bones

1. Esophagus problems.

Some people who take ACTONEL may develop problems in the esophagus (the tube that connects the mouth and the stomach). These problems include irritation, inflammation, or ulcers of the esophagus which may sometimes bleed.

- It is important that you take ACTONEL exactly as prescribed to help lower your chance of getting esophagus problems. (See the section “How should I take ACTONEL?”)
- Stop taking ACTONEL and call your doctor right away if you get chest pain, new or worsening heartburn, or have trouble or pain when you swallow.

2. Low calcium levels in your blood (hypocalcemia).

ACTONEL may lower the calcium levels in your blood. If you have low blood calcium before you start taking ACTONEL, it may get worse during treatment. Your low blood calcium must be treated before you take ACTONEL. Most people with low blood calcium levels do not have symptoms, but some people may have symptoms. Call your doctor right away if you have symptoms of low blood calcium such as:

- Spasms, twitches, or cramps in your muscles
- Numbness or tingling in your fingers, toes, or around your mouth

Your doctor may prescribe calcium and vitamin D to help prevent low calcium levels in your blood, while you take ACTONEL. Take calcium and vitamin D as your doctor tells you to.

3. Severe jaw bone problems (osteonecrosis).

Severe jaw bone problems may happen when you take ACTONEL. Your doctor should examine your mouth before you start ACTONEL. Your doctor may tell you to see your dentist before you start ACTONEL. It is important for you to practice good mouth care during treatment with ACTONEL.

4. Bone, joint, or muscle pain.

Some people who take ACTONEL develop severe bone, joint, or muscle pain.

5. Unusual breaks in thigh and other bones.

Some people have had unusual bone breaks, including the thigh bone, when taking ACTONEL. A break in the thigh bone can feel like a new pain in your hip, groin, or thigh. People taking ACTONEL can also have breaks in other bones.

Call your doctor right away if you have any of these side effects.

What is ACTONEL?

ACTONEL is a prescription medicine used to:

- Treat or prevent osteoporosis in women after menopause. ACTONEL helps increase bone mass and helps reduce the chance of having a spinal or non-spinal fracture (break).
- Increase bone mass in men with osteoporosis.
- Treat or prevent osteoporosis in either men or women who are taking corticosteroid medicines.
- Treat certain men and women who have Paget’s disease of the bone.

It is not known how long ACTONEL works for the treatment and prevention of osteoporosis. You should see your doctor regularly to determine if ACTONEL is still right for you.

ACTONEL is not for use in children.

Who should not take ACTONEL?

Do not take ACTONEL if you:

- Have certain problems with your esophagus, the tube that connects your mouth with your stomach
- Cannot stand or sit upright for at least 30 minutes
- Have low levels of calcium in your blood
- Are allergic to ACTONEL or any of its ingredients. A list of ingredients is at the end of this leaflet.

What should I tell my doctor before taking ACTONEL?

Before you start ACTONEL, be sure to talk to your doctor if you:

- Have problems with swallowing
- Have stomach or digestive problems
- Have low blood calcium
- Plan to have dental surgery or teeth removed
- Have kidney problems
- Have been told you have trouble absorbing minerals in your stomach or intestines (malabsorption syndrome)
- Are pregnant, plan to become pregnant, or suspect that you are pregnant. If you become pregnant while taking ACTONEL, stop taking it and contact your doctor. It is not known if ACTONEL can harm your unborn baby.
- Are breastfeeding or plan to breastfeed. It is not known if ACTONEL passes into your milk and may harm your baby.

Especially tell your doctor if you take:

- antacids
- aspirin
- Nonsteroidal Anti-Inflammatory (NSAID) medicines

Tell your doctor about all the medicines you take, including prescription and non-prescription medicines, vitamins and herbal supplements. Certain medicines may affect how ACTONEL works.

Know the medicines you take. Keep a list of them and show it to your doctor and pharmacist each time you get a new medicine.

How should I take ACTONEL?

- Take ACTONEL exactly as your doctor tells you. Your doctor may change your dose of ACTONEL if needed.
- ACTONEL works only if taken on an empty stomach.
- Take 1 ACTONEL tablet, after you get up for the day and before taking your first food, drink, or other medicine.
- Take ACTONEL while you are sitting or standing.
- Do not chew or suck on a tablet of ACTONEL.
- Swallow ACTONEL tablet with a full glass (6 to 8 ounces) of plain water only.
- Do not take ACTONEL with mineral water, coffee, tea, soda, or juice.

After swallowing ACTONEL tablet, wait at least 30 minutes:

- Before you lie down. You may sit, stand or walk, and do normal activities like reading.
- Before you take your first food or drink except for plain water.
- Before you take other medicines, including antacids, calcium, and other supplements and vitamins.

Do not lie down for at least 30 minutes after you take ACTONEL and after you eat your first food of the day.

If you miss a dose of ACTONEL, do not take it later in the day. Take your missed dose the next morning and then return to your normal schedule. Do not take 2 doses at the same time.

If you miss more than 2 doses of ACTONEL in a month, call your doctor for instructions.

If you take too much ACTONEL, call your doctor. Do not try to vomit. Do not lie down.

What are the possible side effects of ACTONEL?

ACTONEL may cause serious side effects:

- See “What is the most important information I should know about ACTONEL?”

The most common side effects of ACTONEL are:

- pain, including back and joint pain
- stomach area (abdominal) pain
- heartburn

You may get allergic reactions, such as hives, swelling of your face, lips, tongue, or throat.

Tell your doctor if you have any side effect that bothers you or that does not go away.

These are not all the possible side effects of ACTONEL. For more information, ask your doctor or pharmacist.

Call your doctor for medical advice about side effects. You may report side effects to FDA at 1-800-FDA-1088.

How should I store ACTONEL?

- Store ACTONEL at room temperature, 68° F to 77° F (20° C to 25° C).

Safely throw away medicine that is out of date or no longer needed.

Keep ACTONEL and all medicines out of the reach of children.

General information about the safe and effective use of ACTONEL.

Medicines are sometimes prescribed for purposes other than those listed in a Medication Guide. Do not use ACTONEL for a condition for which it was not prescribed. Do not give ACTONEL to other people, even if they have the same symptoms you have. It may harm them.

This Medication Guide summarizes the most important information about ACTONEL. If you would like more information, talk with your doctor. You can ask your doctor or pharmacist for information about ACTONEL that is written for health professionals.

For more information, go to www.Actonel.com or call 1-800-633-9110.

What are the ingredients in ACTONEL?

Active ingredient: risedronate sodium

Inactive ingredients in all dose strengths: crospovidone, hydroxypropyl cellulose, hypromellose, magnesium stearate, microcrystalline cellulose, polyethylene glycol, silicon dioxide, titanium dioxide.

Inactive ingredients specific to a dose strength: 5 mg—ferric oxide yellow, lactose monohydrate; 30 mg—lactose monohydrate; 35 mg—ferric oxide red, ferric oxide yellow, lactose monohydrate; 75 mg—ferric oxide red; 150 mg—FD&C blue #2 aluminum lake.

This Medication Guide has been approved by the U.S. Food and Drug Administration.

Distributed by:
AbbVie Inc.
North Chicago, Illinois 60064

© 2026 AbbVie. All rights reserved.
Actonel and its design are trademarks of Allergan Pharmaceuticals International Limited, an
AbbVie company.

Revised: 02/2026

133169 R1

PACKAGE LABEL

PRINCIPAL DISPLAY PANEL

Rx Only
NDC 0430-0471-15
Actonel
(risedronate sodium) tablets
5 mg
30 Tablets

PACKAGE LABEL

PRINCIPAL DISPLAY PANEL

Rx Only
NDC 0430-0470-15
Actonel
(risedronate sodium) tablets
30 mg
30 Tablets

PACKAGE LABEL

PRINCIPAL DISPLAY PANEL

NDC 0430-0472-03

4 Week Supply
(4 tablets)
Dispense the enclosed
Medication Guide
to each patient
Actonel®
(risedronate sodium) tablets
35 mg
Once-a-Week
4 tablets

PACKAGE LABEL

PRINCIPAL DISPLAY PANEL

NDC 0430-0477-02
Actonel
(risedronate sodium) tablets
75 mg
One Month Pack
(2 tablets)
Rx Only

PACKAGE LABEL

PRINCIPAL DISPLAY PANEL

NDC 0430-0478-01
One Month Pack
(1 tablet)
Dispense the enclosed
Medication Guide
to each patient
Actonel®
(risedronate sodium) tablets
150 mg
Once-a-Month
1 tablet